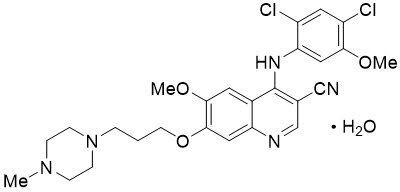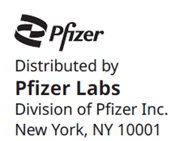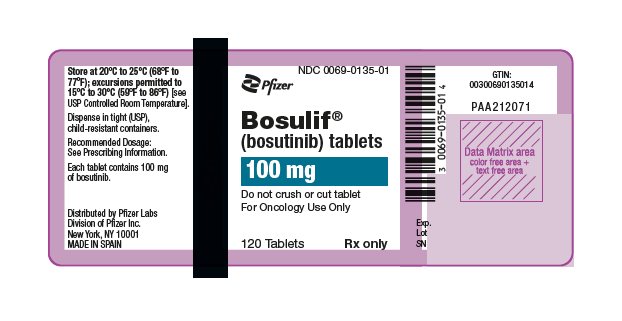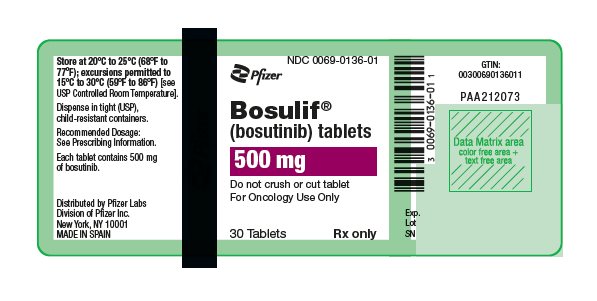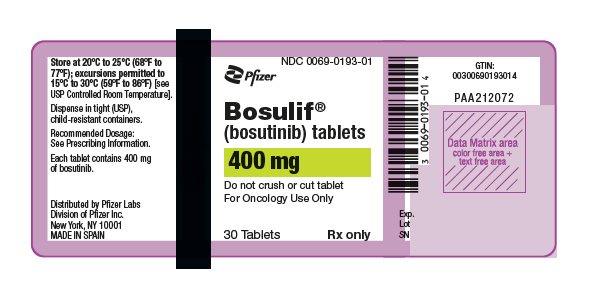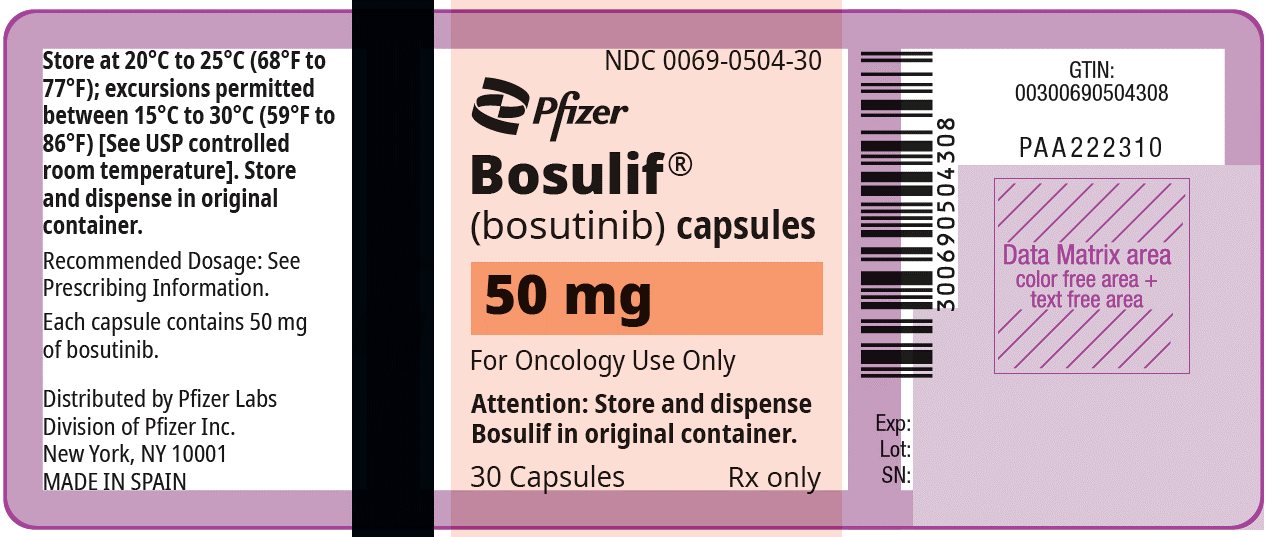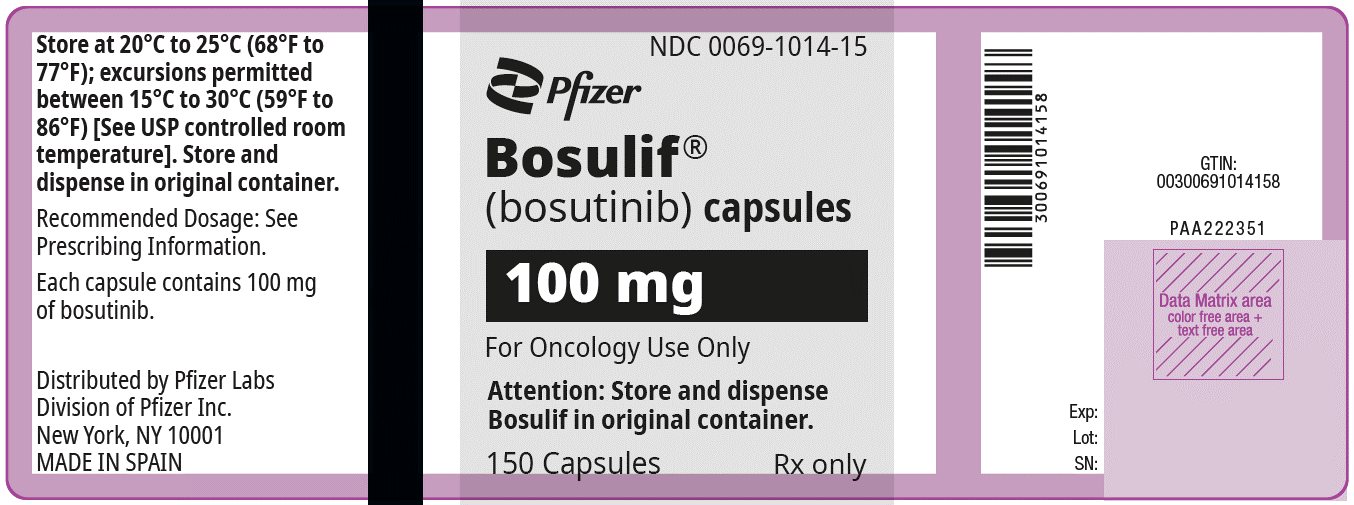 DRUG LABEL: BOSULIF
NDC: 0069-0135 | Form: TABLET, FILM COATED
Manufacturer: Pfizer Laboratories Div Pfizer Inc
Category: prescription | Type: HUMAN PRESCRIPTION DRUG LABEL
Date: 20241213

ACTIVE INGREDIENTS: BOSUTINIB MONOHYDRATE 100 mg/1 1
INACTIVE INGREDIENTS: MICROCRYSTALLINE CELLULOSE; CROSCARMELLOSE SODIUM; POVIDONE K25; MAGNESIUM STEARATE; POLYVINYL ALCOHOL, UNSPECIFIED; TITANIUM DIOXIDE; POLYETHYLENE GLYCOL 3350; TALC; FERRIC OXIDE YELLOW; POLOXAMER 188

HIGHLIGHTS OF PRESCRIBING INFORMATION

These highlights do not include all the information needed to use BOSULIF safely and effectively. See full prescribing information for BOSULIF.
BOSULIF® (bosutinib) tablets, for oral use
BOSULIF® (bosutinib) capsules, for oral use
Initial U.S. Approval: 2012

1 INDICATIONS AND USAGE

BOSULIF is a kinase inhibitor indicated for the treatment of

- adult and pediatric patients 1 year of age and older with chronic phase Ph+ chronic myelogenous leukemia (CML), newly-diagnosed or resistant or intolerant to prior therapy. (1)
- adult patients with accelerated, or blast phase Ph+ CML with resistance or intolerance to prior therapy. (1)

2 DOSAGE AND ADMINISTRATION

- Adult patients with newly-diagnosed chronic phase Ph+ CML: 400 mg orally once daily with food. (2.1)
- Adult patients with chronic, accelerated, or blast phase Ph+ CML with resistance or intolerance to prior therapy: 500 mg orally once daily with food. (2.1)
- Pediatric patients with newly-diagnosed chronic phase Ph+ CML: 300 mg/m^2 orally once daily with food. (2.1)
- Pediatric patients with chronic phase Ph+ CML with resistance or intolerance to prior therapy: 400 mg/m^2 orally once daily with food. (2.1)
- Consider dose escalation by increments of 100 mg once daily to a maximum of 600 mg daily in adult patients who do not reach complete hematologic, cytogenetic, or molecular response and do not have Grade 3 or greater adverse reactions. (2.2)
- Consider dose escalation by increments of 50 mg for those with a BSA <1.1 m^2 and 100 mg for those with a BSA ≥1.1 m^2 to a maximum of 600 mg daily in pediatric patients who do not reach sufficient response after 3 months. (2.2)
- Adjust dosage for toxicity and organ impairment (2)

3 DOSAGE FORMS AND STRENGTHS

- Tablets: 100 mg, 400 mg, and 500 mg. (3)
- Capsules 50 mg, 100 mg. (3)

4 CONTRAINDICATIONS

Hypersensitivity to BOSULIF. (4)

5 WARNINGS AND PRECAUTIONS

- Gastrointestinal Toxicity: Monitor and manage as necessary. Withhold, dose reduce, or discontinue BOSULIF. (2.3, 5.1)
- Myelosuppression: Monitor blood counts and manage as necessary. Withhold, dose reduce, or discontinue BOSULIF. (2.4, 5.2)
- Hepatic Toxicity: Monitor liver enzymes at least monthly for the first 3 months and as needed. Withhold, dose reduce, or discontinue BOSULIF. (2.3, 5.3)
- Cardiovascular Toxicity: Monitor and manage as necessary. Interrupt, dose reduce, or discontinue BOSULIF. (5.4)
- Fluid Retention: Monitor patients and manage using standard of care treatment. Interrupt, dose reduce, or discontinue BOSULIF. (2.3, 5.5)
- Renal Toxicity: Monitor patients for renal function at baseline and during therapy with BOSULIF. (5.6)
- Embryo-Fetal Toxicity: BOSULIF can cause fetal harm. Advise female patients of reproductive potential of potential risk to a fetus and to use effective contraception. (5.7)

6 ADVERSE REACTIONS

- Most common adverse reactions (≥20%), in adult and pediatric patients with CML are diarrhea, abdominal pain, vomiting, nausea, rash, fatigue, hepatic dysfunction, headache, pyrexia, decreased appetite respiratory tract infection, and constipation. The most common laboratory abnormalities (≥20%) in adult and pediatric patients are creatinine increased, hemoglobin decreased, lymphocyte count decreased, platelets decreased, ALT increased, calcium decreased, white blood cell count decreased, AST increased, absolute neutrophil count decreased, glucose increased, phosphorus decreased, urate increased, alkaline phosphatase increased, lipase increased, creatine kinase increased, and amylase increased. (6.1)

To report SUSPECTED ADVERSE REACTIONS, contact Pfizer Inc. at 1-800-438-1985 or FDA at 1-800-FDA-1088 or www.fda.gov/medwatch.

7 DRUG INTERACTIONS

- Strong and Moderate CYP3A Inhibitors: Avoid concomitant use with BOSULIF. (7.1)
- Strong CYP3A Inducers: Avoid concomitant use with BOSULIF. (7.1)
- Proton Pump Inhibitors: Use short-acting antacids or H2 blockers as an alternative to proton pump inhibitors. (7.1)

8 USE IN SPECIFIC POPULATIONS

Lactation: Advise women not to breastfeed. (8.2)

FULL PRESCRIBING INFORMATION

1 INDICATIONS AND USAGE

BOSULIF is indicated for the treatment of:

- Adult and pediatric patients 1 year of age and older with chronic phase (CP) Philadelphia chromosome-positive chronic myelogenous leukemia (Ph+ CML), newly-diagnosed or resistant or intolerant to prior therapy [see Clinical Studies (14.1, 14.2, 14.3)].
- Adult patients with accelerated phase (AP), or blast phase (BP) Ph+ CML with resistance or intolerance to prior therapy [see Clinical Studies (14.2)].

2 DOSAGE AND ADMINISTRATION

2.1 Recommended Dosage

The recommended dosage is taken orally once daily with food. Swallow tablets whole. Do not cut, crush, break or chew tablets. Continue treatment with BOSULIF until disease progression or intolerance to therapy.

Capsules may be swallowed whole. For patients who are unable to swallow a whole capsule(s), each capsule can be opened and the contents mixed with applesauce or yogurt. Mixing the capsule contents with applesauce or yogurt cannot be considered a substitute of a proper meal.

If a dose is missed beyond 12 hours, the patient should skip the dose and take the usual prescribed dose on the following day.

Dosage in Adult Patients with Newly-Diagnosed CP Ph+ CML

The recommended dosage of BOSULIF is 400 mg orally once daily with food.

Dosage in Adult Patients with CP, AP, or BP Ph+ CML with Resistance or Intolerance to Prior Therapy

The recommended dosage of BOSULIF is 500 mg orally once daily with food.

Dosage in Pediatric Patients with Newly-Diagnosed CP Ph+ CML or with CP Ph+ CML with Resistance or Intolerance to Prior Therapy

The recommended dose of BOSULIF for pediatric patients with newly-diagnosed CP Ph+ CML is 300 mg/m^2 orally once daily with food and the recommended dosage for pediatric patients with CP Ph+ CML that is resistant or intolerant to prior therapy is 400 mg/m^2 orally once daily with food and dose recommendations are provided in Table 1. As appropriate, the desired dose can be attained by combining different strengths of BOSULIF tablets or capsules.

Table 1: Dosing of BOSULIF for Pediatric Patients with Newly-Diagnosed CP Ph+ CML or with CP Ph+ CML with Resistance or Intolerance to Prior Therapy
BSA [BSA=Body Surface Area] | Newly-Diagnosed Recommended Dose; (Once Daily) | Resistant or Intolerant Recommended Dose; (Once Daily)
< 0.55 m^2 | 150 mg | 200 mg
0.55 to < 0.63 m^2 | 200 mg | 250 mg
0.63 to < 0.75 m^2 | 200 mg | 300 mg
0.75 to < 0.9 m^2 | 250 mg | 350 mg
0.9 to < 1.1 m^2 | 300 mg | 400 mg
≥ 1.1 m^2 | 400 mg [maximum starting dose (corresponding to maximum starting dose in adult indication)] | 500 mg

Preparation Instructions for BOSULIF Capsules Mixed with Applesauce or Yogurt

For patients who are unable to swallow capsules, the contents of the capsules can be mixed with applesauce or yogurt. Remove the required number of capsules from the container to prepare the dose as instructed and the amount of either room temperature applesauce or yogurt in a clean container. Carefully open each capsule, add the entire capsule content of each capsule into the applesauce or yogurt, then mix the entire dose into the applesauce or yogurt. Patients should immediately consume the full mixture in its entirety, without chewing. Do not store the mixture for later use. If the entire preparation is not swallowed do not take an additional dose. Wait until the next day to resume dosing.

Table 2: BOSULIF Dose Using Capsules and Soft Food Volumes
Dose | Volume of Applesauce or Yogurt
100 mg | 10 mL (2 teaspoons)
150 mg | 15 mL (3 teaspoons)
200 mg | 20 mL (4 teaspoons)
250 mg | 25 mL (5 teaspoons)
300 mg | 30 mL (6 teaspoons)
350 mg | 30 mL (6 teaspoons)
400 mg | 35 mL (7 teaspoons)
450 mg | 40 mL (8 teaspoons)
500 mg | 45 mL (9 teaspoons)
550 mg | 45 mL (9 teaspoons)
600 mg | 50 mL (10 teaspoons)

2.2 Dose Escalation

In clinical studies of adult patients with Ph+ CML, dose escalation by increments of 100 mg once daily to a maximum of 600 mg once daily was allowed in patients who did not achieve or maintain a hematologic, cytogenetic, or molecular response and who did not have Grade 3 or higher adverse reactions at the recommended starting dosage.

In pediatric patients with BSA <1.1 m^2 and an insufficient response after 3 months consider increasing dose by 50 mg increments up to maximum of 100 mg above starting dose. Dose increases for insufficient response in pediatric patients with BSA ≥1.1 m^2 can be conducted similarly to adult recommendations in 100 mg increments.

The maximum dose in pediatric and adult patients is 600 mg once daily.

2.3 Dosage Adjustments for Non-Hematologic Adverse Reactions

Elevated liver transaminases: If elevations in liver transaminases greater than 5×institutional upper limit of normal (ULN) occur, withhold BOSULIF until recovery to less than or equal to 2.5×ULN and resume at 400 mg once daily thereafter. If recovery takes longer than 4 weeks, discontinue BOSULIF. If transaminase elevations greater than or equal to 3×ULN occur concurrently with bilirubin elevations greater than 2×ULN and alkaline phosphatase less than 2×ULN (Hy's law case definition), discontinue BOSULIF [see Warnings and Precautions (5.3)].

Diarrhea: For National Cancer Institute Common Terminology Criteria for Adverse Events (NCI CTCAE) Grade 3–4 diarrhea (increase of greater than or equal to 7 stools/day over baseline/pretreatment), withhold BOSULIF until recovery to Grade less than or equal to 1. BOSULIF may be resumed at 400 mg once daily [see Warnings and Precautions (5.1)].

For other clinically significant, moderate or severe non-hematological toxicity, withhold BOSULIF until the toxicity has resolved, then consider resuming BOSULIF at a dose reduced by 100 mg taken once daily. If clinically appropriate, consider re-escalating the dose of BOSULIF to the starting dose taken once daily.

In pediatric patients, dose adjustments for non-hematologic toxicities can be conducted similarly to adults, however the dose reduction increments may differ. For pediatric patients with BSA <1.1 m^2, reduce dose by 50 mg initially followed by additional 50 mg increment if the adverse reaction (AR) persists. For pediatric patients with BSA ≥1.1 m^2 or greater, reduce dose similarly to adults.

2.4 Dosage Adjustments for Myelosuppression

Dose reductions for severe or persistent neutropenia and thrombocytopenia are described below (Table 3).

Table 3: Dose Adjustments for Neutropenia and Thrombocytopenia in Adult and Pediatric Patients
ANC [Absolute Neutrophil Count] less than 1000×10^6/L; or; Platelets less than 50,000×10^6/L | Withhold BOSULIF until ANC greater than or equal to1000×10^6/L and platelets greater than or equal to 50,000×10^6/L.; Resume treatment with BOSULIF at the same dose if recovery occurs within 2 weeks. If blood counts remain low for greater than 2 weeks, upon recovery, reduce dose by 100 mg and resume treatment, or by 50 mg in pediatric patients with BSA <1.1 m^2 and resume treatment.; If cytopenia recurs, reduce dose by an additional 100 mg upon recovery and resume treatment, or by an additional 50 mg in pediatric patients with BSA <1.1 m^2 and resume treatment.

2.5 Dosage Adjustments for Renal Impairment or Hepatic Impairment

The recommended starting doses for patients with renal and hepatic impairment are described in Table 4 below.

Table 4: Dose Adjustments for Renal and Hepatic Impairment in Adult Patients
 |  | Recommended Starting Dosage
 |  | Newly-diagnosed chronic phase Ph+ CML | Chronic, accelerated, or blast phase Ph+ CML with resistance or intolerance to prior therapy
Normal renal and hepatic function |  | 400 mg daily | 500 mg daily
Renal impairment
 | Creatinine clearance 30 to 50 mL/min | 300 mg daily | 400 mg daily
 | Creatinine clearance less than 30 mL/min | 200 mg daily | 300 mg daily
Hepatic impairment
 | Mild (Child-Pugh A), Moderate (Child-Pugh B) or Severe (Child-Pugh C) | 200 mg daily | 200 mg daily
[see Use in Specific Populations (8.6, 8.7) and Clinical Pharmacology (12.3)].

Table 5: Dosage Adjustments for Renal and Hepatic Impairment in Pediatric Patients
 | Newly-Diagnosed CP Ph+ CML Recommended Starting Dose (Once Daily) By Organ Function
Pediatric Patients by Separated BSA [BSA=Body Surface Area] Band | Normal renal and hepatic function | Renal Impairment: Creatinine clearance 30 to 50 mL/min | Renal Impairment: Creatinine clearance less than 30 mL/min | Hepatic Impairment: Mild (Child-Pugh A), Moderate (Child-Pugh B) or Severe (Child-Pugh C)
Pediatric < 0.55 m^2 | 150 mg | 100 mg | 100 mg | 100 mg
Pediatric 0.55 to < 0.63 m^2 | 200 mg | 150 mg | 100 mg | 100 mg
Pediatric 0.63 to < 0.75 m^2 | 200 mg | 150 mg | 100 mg | 100 mg
Pediatric 0.75 to < 0.9 m^2 | 250 mg | 200 mg | 150 mg | 100 mg
Pediatric 0.9 to < 1.1 m^2 | 300 mg | 200 mg | 200 mg | 150 mg
Pediatric ≥ 1.1 m^2 | 400 mg | 300 mg | 200 mg | 200 mg
 | CP Ph+ CML with Resistance or Intolerance to Prior Therapy Recommended Starting Dose (Once Daily) By Organ Function
Pediatric Patients by Separated BSA Band | Normal renal and hepatic function | Renal Impairment: Creatinine clearance 30 to 50 mL/min | Renal Impairment: Creatinine clearance less than 30 mL/min | Hepatic Impairment: Mild (Child-Pugh A), Moderate (Child-Pugh B) or Severe (Child-Pugh C)
Pediatric < 0.55 m^2 | 200 mg | 150 mg | 100 mg | 100 mg
Pediatric 0.55 to < 0.63 m^2 | 250 mg | 200 mg | 150 mg | 100 mg
Pediatric 0.63 to < 0.75 m^2 | 300 mg | 200 mg | 200 mg | 150 mg
Pediatric 0.75 to < 0.9 m^2 | 350 mg | 250 mg | 200 mg | 150 mg
Pediatric 0.9 to < 1.1 m^2 | 400 mg | 300 mg | 250 mg | 200 mg
Pediatric ≥ 1.1 m^2 | 500 mg | 400 mg | 300 mg | 200 mg
[see Use in Specific Populations (8.6, 8.7) and Clinical Pharmacology (12.3)].

3 DOSAGE FORMS AND STRENGTHS

Tablets:

- 100 mg: yellow, oval, biconvex, film-coated tablets debossed with "Pfizer" on one side and "100" on the other.
- 400 mg: orange, oval, biconvex, film-coated tablets debossed with "Pfizer" on one side and "400" on the other.
- 500 mg: red, oval, biconvex, film-coated tablets debossed with "Pfizer" on one side and "500" on the other.

Capsules:

- 50 mg: white body/orange cap with “BOS 50” printed on the body and “Pfizer” printed on the cap in black ink.
- 100 mg: white body/brownish-red cap with “BOS 100” printed on the body and “Pfizer” printed on the cap in black ink.

4 CONTRAINDICATIONS

BOSULIF is contraindicated in patients with a history of hypersensitivity to BOSULIF. Reactions have included anaphylaxis [see Adverse Reactions (6.1)].

5 WARNINGS AND PRECAUTIONS

5.1 Gastrointestinal Toxicity

Diarrhea, nausea, vomiting, and abdominal pain occur with BOSULIF treatment. Monitor and manage patients using standards of care, including antidiarrheals, antiemetics, and fluid replacement.

In the randomized clinical trial in adult patients with newly-diagnosed Ph+ CML, the median time to onset for diarrhea (all grades) was 4 days and the median duration per event was 3 days.

Among 546 adult patients in a single-arm study in patients with CML who were resistant or intolerant to prior therapy, the median time to onset for diarrhea (all grades) was 2 days and the median duration per event was 2 days. Among the patients who experienced diarrhea, the median number of episodes of diarrhea per patient during treatment with BOSULIF was 3 (range 1–268).

Among 49 pediatric patients with newly-diagnosed CP Ph+ CML or who had CP Ph+ CML that was resistant or intolerant to prior therapy, the median time to onset for diarrhea (all grades) was 2 days and the duration was 2 days. Among patients who experienced diarrhea, the median number of episodes of diarrhea per patient during treatment with BOSULIF was 2 (range 1 – 198).

To manage gastrointestinal toxicity, withhold, dose reduce, or discontinue BOSULIF as necessary [see Dosage and Administration (2.3) and Adverse Reactions (6)].

5.2 Myelosuppression

Thrombocytopenia, anemia and neutropenia occur with BOSULIF treatment. Perform complete blood counts weekly for the first month of therapy and then monthly thereafter, or as clinically indicated. To manage myelosuppression, withhold, dose reduce, or discontinue BOSULIF as necessary [see Dosage and Administration (2.4) and Adverse Reactions (6)].

5.3 Hepatic Toxicity

Bosutinib may cause elevations in serum transaminases (alanine aminotransferase [ALT], aspartate aminotransferase [AST]).

Two cases consistent with drug induced liver injury (defined as concurrent elevations in ALT or AST greater than or equal to 3×ULN with total bilirubin greater than 2×ULN and alkaline phosphatase less than 2×ULN) have occurred without alternative causes. This represented 2 out 1711 patients in BOSULIF clinical trials.

In the 268 adult patients from the safety population in the randomized clinical trial in patients with newly-diagnosed CML in the BOSULIF treatment group, the incidence of ALT elevation was 68.3% and increased AST was 56%. Of patients who experienced increased transaminases of any grade, 73% experienced their first increase within the first 3 months. The median time to onset of increased ALT and AST was 29 and 56 days, respectively, and the median duration was 19 and 15 days, respectively.

Among the 546 adult patients in a single-arm study in patients with CML who were resistant or intolerant to prior therapy, the incidence of increased ALT was 53.3% and AST elevation was 46.7%. Sixty percent of the patients experienced an increase in either ALT or AST. Most cases of transaminase elevations in this study occurred early in treatment; of patients who experienced increased transaminases of any grade, more than 81% experienced their first increase within the first 3 months. The median time to onset of increased ALT and AST was 22 and 29 days, respectively, and the median duration for each was 21 days.

Among 49 pediatric patients with newly‑diagnosed CP Ph+ CML or who had CP Ph+ CML that was resistant or intolerant to prior therapy, the incidence based on laboratory data that worsened from baseline of increased ALT was 59% and of increased AST 51%. Seventy-six percent of the patients experienced an increase in either ALT or AST. Most cases of increased transaminases occurred early in treatment; of patients who experienced increased transaminases of any grade, 84% of patients experienced their first increases within the first 3 months. The median time to onset for adverse reactions of increased ALT and AST was 22 and 15 days, respectively. The median duration for adverse reactions of Grade 3 or 4 increased ALT or AST was 26 and 12 days, respectively.

Perform hepatic enzyme tests monthly for the first 3 months of BOSULIF treatment and as clinically indicated. In patients with transaminase elevations, monitor liver enzymes more frequently. Withhold, dose reduce, or discontinue BOSULIF as necessary [see Dosage and Administration (2.3) and Adverse Reactions (6)].

5.4 Cardiovascular Toxicity

BOSULIF can cause cardiovascular toxicity including cardiac failure, left ventricular dysfunction, and cardiac ischemic events. Cardiac failure events occurred more frequently in previously treated patients than in patients with newly diagnosed CML and were more frequent in patients with advanced age or risk factors, including previous medical history of cardiac failure. Cardiac ischemic events occurred in both previously treated patients and in patients with newly diagnosed CML and were more common in patients with coronary artery disease risk factors, including history of diabetes, body mass index greater than 30, hypertension, and vascular disorders.

In a randomized study of adult patients with newly diagnosed CML, cardiac failure occurred in 1.9% of patients treated with BOSULIF compared to 0.8% of patients treated with imatinib. Cardiac ischemic events occurred in 4.9% of patients treated with BOSULIF compared to 0.8% of patients treated with imatinib.

In a single-arm study in adult patients with CML who were resistant or intolerant to prior therapy, cardiac failure was observed in 5.3% of patients and cardiac ischemic events were observed in 5.1% of patients treated with BOSULIF.

Among 49 pediatric patients with newly diagnosed CP Ph+ CML or who had CP Ph+ CML that was resistant or intolerant to prior therapy, 4 (8%) patients had Grade 1-2 cardiac events, including tachycardia (n=2), angina pectoris, right bundle branch block, and sinus tachycardia (n=1 each).

Monitor patients for signs and symptoms consistent with cardiac failure and cardiac ischemia and treat as clinically indicated. Interrupt, dose reduce, or discontinue BOSULIF as necessary [see Dosage and Administration (2.3) and Adverse Reactions (6)].

5.5 Fluid Retention

Fluid retention occurs with BOSULIF and may manifest as pericardial effusion, pleural effusion, pulmonary edema, and/or peripheral edema.

In the randomized clinical trial of 268 adult patients with newly-diagnosed CML in the bosutinib treatment group, 3 patients (1.1%) experienced severe fluid retention of Grade 3, 1 patient experienced Grade 3 pericardial effusion, and 2 patients experienced Grade 3 pleural effusion. Among 546 adult patients in a single-arm study in patients with Ph+ CML who were resistant or intolerant to prior therapy, Grade 3 or 4 fluid retention was reported in 30 patients (6%). Some patients experienced more than one fluid retention event. Specifically, 24 patients experienced Grade 3 or 4 pleural effusions, 9 patients experienced Grade 3 or Grade 4 pericardial effusions, and 6 patients experienced Grade 3 edema.

Among 49 pediatric patients with newly diagnosed CP Ph+ CML or who had CP Ph+ CML that was resistant or intolerant to prior therapy, Grade 1-2 pericardial effusion, peripheral edema, and face edema were reported in 1 patient each.

Monitor and manage patients using standards of care. Interrupt, dose reduce or discontinue BOSULIF as necessary [see Dosage and Administration (2.3) and Adverse Reactions (6)].

5.6 Renal Toxicity

An on-treatment decline in estimated glomerular filtration rate (eGFR) has occurred in patients treated with BOSULIF. Table 6 identifies the shift from baseline to lowest observed eGFR during BOSULIF therapy for patients in the pooled leukemia studies regardless of line of therapy. The median duration of therapy with BOSULIF was approximately 24 months (range, 0.03 to 155) for patients in these studies.

Table 6: Shift From Baseline to Lowest Observed eGFR Group During Treatment Safety Population in Clinical Studies (N=1372) [Among the 1372 patients, eGFR was missing in 7 patients at baseline or on-therapy. There were no patients with kidney failure at baseline.]
Baseline |  | Follow-Up
Renal Function Status | N | Normal n (%) | Mild n (%) | Mild to Moderate n (%) | Moderate to Severe n (%) | Severe n (%) | Kidney Failure n (%)
Normal | 527 | 115 (21.8) | 330 (62.6) | 50 (9.5) | 23 (4.4) | 3 (0.6) | 5 (0.9)
Mild | 672 | 10 (1.5) | 259 (38.5) | 271 (40.3) | 96 (14.3) | 26 (3.9) | 6 (0.9)
Mild to Moderate | 137 | 0 | 6 (4.4) | 40 (29.2) | 66 (48.2) | 24 (17.5) | 1 (0.7)
Moderate to Severe | 33 | 0 | 1 (3.0) | 1 (3.0) | 8 (24.2) | 19 (57.6) | 4 (12.1)
Severe | 1 | 0 | 0 | 0 | 0 | 0 | 1 (100)
Total | 1370 | 125 (9.1) | 596 (43.5) | 362 (26.4) | 193 (14.1) | 72 (5.2) | 17 (1.2)
Abbreviations: eGFR=estimated glomerular filtration rate; N/n=number of patients.
Notes: eGFR was calculated using Modification in Diet in Renal Disease method (MDRD).
Notes: Grading is based on Kidney Disease Improving Global Outcomes (KDIGO) Classification by eGFR: Normal: greater than or equal to 90, Mild: 60 to less than 90, Mild to Moderate: 45 to less than 60, Moderate to Severe: 30 to less than 45, Severe: 15 to less than 30, Kidney Failure: less than 15 ml/min/1.73 m^2.

Overall, 45% of the pediatric patients with newly diagnosed CP Ph+ CML or resistant or intolerant CP Ph+ CML who had normal eGFR at baseline shifted to a maximum of mild, and 40% pediatric patients who had mild eGFR at baseline shifted to a maximum of moderate during treatment.

Monitor renal function at baseline and during therapy with BOSULIF, with particular attention to those patients who have preexisting renal impairment or risk factors for renal dysfunction. Consider dose adjustment in patients with baseline and treatment emergent renal impairment [see Dosage and Administration (2.5)].

5.7 Embryo-Fetal Toxicity

Based on findings from animal studies and its mechanism of action, BOSULIF can cause fetal harm when administered to a pregnant woman. There are no available data in pregnant women to inform the drug-associated risk. In animal reproduction studies conducted in rats and rabbits, oral administration of bosutinib during organogenesis caused adverse developmental outcomes, including structural abnormalities, embryo-fetal mortality, and alterations to growth at maternal exposures (AUC) as low as 1.2 times the human exposure at the dose of 500 mg/day. Advise pregnant women of the potential risk to a fetus. Advise females of reproductive potential to use effective contraception during treatment and for 2 weeks after the last dose [see Use in Specific Populations (8.1, 8.3) and Clinical Pharmacology (12.1)].

6 ADVERSE REACTIONS

The following clinically significant adverse reactions are discussed in greater detail in other sections of the labeling:

- Gastrointestinal toxicity [see Warnings and Precautions (5.1)].
- Myelosuppression [see Warnings and Precautions (5.2)].
- Hepatic toxicity [see Warnings and Precautions (5.3)].
- Cardiovascular toxicity [see Warnings and Precautions (5.4)].
- Fluid retention [see Warnings and Precautions (5.5)].
- Renal toxicity [see Warnings and Precautions (5.6)].

6.1 Clinical Trials Experience

Because clinical trials are conducted under widely varying conditions, adverse reaction rates observed in the clinical trials of a drug cannot be directly compared to rates in the clinical trials of another drug and may not reflect the rates observed in practice.

The most common adverse reactions, in ≥20% of adults with newly diagnosed CP Ph+ CML or CP, AP, or BP Ph+ CML with resistance or intolerance to prior therapy (N=814) were diarrhea (80%), rash (44%), nausea (44%), abdominal pain (43%), vomiting (33%), fatigue (33%), hepatic dysfunction (33%), respiratory tract infection (25%), pyrexia (24%), and headache (21%).

The most common laboratory abnormalities that worsened from baseline in ≥20% of adults were creatinine increased (93%), hemoglobin decreased (90%), lymphocyte count decreased (72%), platelets decreased (69%), ALT increased (58%), calcium decreased (53%), white blood cell count decreased (52%), absolute neutrophils count decreased (50%), AST increased (50%), glucose increased (46%), phosphorus decreased (44%), urate increased (41%), alkaline phosphatase increased (40%), lipase increased (36%), creatine kinase increased (29%), and amylase increased (24%).

The most common adverse reactions, in ≥20% of pediatric patients (N=49) were diarrhea (82%), abdominal pain (73%), vomiting (55%), nausea (49%), rash (49%), fatigue (37%), hepatic dysfunction (37%), headache (35%), pyrexia (31%), decreased appetite (27%), and constipation (20%).

The most common laboratory abnormalities that worsened from baseline in ≥20% of pediatric patients were creatinine increased (92%), alanine aminotransferase increased (59%), white blood cell count decreased (53%), aspartate aminotransferase increased (51%), platelet count decreased (49%), glucose increased (41%), calcium decreased (31%), hemoglobin decreased (31%), neutrophil count decreased (31%), lymphocyte count decreased (29%), serum amylase increased (27%), and CPK increased (25%).

Adverse Reactions in Adult Patients With Newly-Diagnosed CP CML

The clinical trial randomized and treated 533 patients with newly-diagnosed CP CML to receive BOSULIF 400 mg daily or imatinib 400 mg daily as single agents (Newly-Diagnosed CP CML Study) [see Clinical Studies (14.1)]. The safety population (received at least 1 dose of BOSULIF) included:

- two hundred sixty-eight (268) patients with newly-diagnosed CP CML had a median duration of BOSULIF treatment of 55 months (range: 0.3 to 60 months) and a median dose intensity of 394 mg/day.

Serious adverse reactions occurred in 22% of patients with newly-diagnosed CP CML who received bosutinib. Serious adverse reactions reported in >2% of patients included hepatic dysfunction (4.1%), pneumonia (3.4%), coronary artery disease (3.4%), and gastroenteritis (2.2%). Fatal adverse reactions occurred in 3 patients (1.1%) due to coronary artery disease (0.4%), cardiac failure acute (0.4%), and renal failure (0.4%).

Permanent discontinuation of bosutinib due to an adverse reaction occurred in 20% of patients with newly-diagnosed CP CML who received bosutinib. Adverse reactions which resulted in permanent discontinuation in > 2% of patients included hepatic dysfunction (9%).

Dose modifications (dose interruption or reductions) of bosutinib due to an adverse reaction occurred in 68% of patients with newly-diagnosed CP CML. Adverse reactions which required dose interruptions or reductions in >5% of patients included hepatic dysfunction (27%), thrombocytopenia (16%), diarrhea (16%), lipase increased (10%), neutropenia (7%), abdominal pain (6%), rash (5%).

The most common adverse reactions, in >20% of bosutinib-treated patients with newly-diagnosed CML (N=268) were diarrhea (75%), hepatic dysfunction (45%), rash (40%), abdominal pain (39%), nausea (37%), fatigue (33%), respiratory tract infection (27%), headache (22%), and vomiting (21%).

The most common laboratory abnormalities that worsened from baseline in ≥20% of patients were creatinine increased (94%), hemoglobin decreased (89%), lymphocyte count decreased (84%), ALT increased (68%), platelet count decreased (68%), glucose increased (57%), AST increased (56%), calcium decreased (55%), phosphorus decreased (54%), lipase increased (53%), white blood cell count decreased (50%), absolute neutrophil count decreased (42%), alkaline phosphatase increased (41%), creatine kinase increased (36%), and amylase increased (32%).

Table 7 identifies adverse reactions greater than or equal to 10% for All Grades and Grades 3 or 4 (3/4) for the Phase 3 CP CML safety population.

Table 7: Adverse Reactions (10% or Greater) in Patients With Newly-Diagnosed CML in Bosutinib 400 mg Study [Based on a Minimum of 57 Months of Follow-up. Adverse drug reactions are based on all-causality treatment-emergent adverse events. The commonality stratification is based on 'All Grades' under Total column. 'Grade 3', 'Grade 4' columns indicate maximum toxicity.]
 |  | Bosutinib 400 mg Chronic Phase CML (N=268) |  | Imatinib 400 mg Chronic Phase CML (N=265)
System Organ Class | Preferred Term | All Grades % | Grade 3/4 % | All Grades % | Grade 3/4 %
Gastrointestinal disorders | Diarrhea | 75 | 9 | 40 | 1
 | Abdominal pain [Abdominal pain includes the following preferred terms: Abdominal discomfort, Abdominal pain, Abdominal pain lower, Abdominal pain upper, Abdominal tenderness, Dyspepsia, Epigastric discomfort, Gastrointestinal pain.] | 39 | 2 | 27 | 1
 | Nausea | 37 | 0 | 42 | 0
 | Vomiting | 21 | 1 | 20 | 0
 | Constipation | 13 | 0 | 6 | 0
Hepatobiliary disorders | Hepatic dysfunction [Hepatic dysfunction includes the preferred terms: Alanine aminotransferase increased, Aspartate aminotransferase, Aspartate aminotransferase increased, Bilirubin conjugated increased, Blood alkaline phosphatase increased, Blood bilirubin increased, Drug-induced liver injury, Gamma-glutamyltransferase increased, Hepatic enzyme increased, Hepatic steatosis, Hepatitis, Hepatitis toxic, Hepatocellular injury, Hepatotoxicity, Hyperbilirubinemia, Jaundice, Liver disorder, Liver function test increased, Ocular icterus, Transaminases increased.] | 45 | 27 | 15 | 4
Skin and subcutaneous tissue disorders | Rash [Rash includes the following preferred terms: Acne, Blister, Dermatitis, Dermatitis acneiform, Dermatitis bullous, Dermatitis exfoliative generalized, Drug reaction with eosinophilia and systemic symptoms, Dyshidrotic eczema, Eczema, Eczema asteatotic, Erythema, Erythema nodosum, Genital rash, Lichen planus, Perivascular dermatitis, Photosensitivity reaction, Psoriasis, Rash, Rash erythematous, Rash macular, Rash maculo-papular, Rash papular, Rash pruritic, Rash pustular, Rash vesicular, Seborrhoeic keratosis, Skin discoloration, Skin exfoliation, Skin hypopigmentation, Skin irritation, Skin lesion, Stasis dermatitis.] | 40 | 2 | 30 | 2
 | Pruritus | 11 | <1 | 4 | 0
General disorders and administration-site conditions | Fatigue [Fatigue includes the following preferred terms: Asthenia, Fatigue, Malaise.] | 33 | 1 | 30 | <1
 | Pyrexia | 17 | 1 | 11 | 0
 | Edema [Edema includes the following preferred terms: Eye edema, Eyelid edema, Face edema, Edema, Edema peripheral, Orbital edema, Periorbital edema, Periorbital swelling, Peripheral swelling, Swelling, Swelling face, Swelling of eyelid, Swollen tongue.] | 15 | 0 | 46 | 2
Infections and infestations | Respiratory tract infection [Respiratory tract infection includes the following preferred terms: Nasopharyngitis, Respiratory tract congestion, Respiratory tract infection, Respiratory tract infection viral, Upper respiratory tract infection.] | 27 | 1 | 25 | <1
Nervous system disorders | Headache | 22 | 1 | 15 | 1
Musculoskeletal and connective tissue disorders | Arthralgia | 18 | 1 | 18 | <1
 | Back pain | 12 | <1 | 9 | <1
Respiratory, thoracic, and mediastinal disorders | Cough | 11 | 0 | 10 | 0
 | Dyspnea | 11 | 1 | 6 | 1
Metabolism and nutrition disorders | Decreased appetite | 11 | <1 | 6 | 0
Vascular disorders | Hypertension [Hypertension* includes the preferred terms: Blood pressure systolic increased, Hypertension, Hypertensive crisis, Hypertensive heart disease, Retinopathy hypertensive.] | 10 | 5 | 11 | 5

In the randomized study in patients with newly-diagnosed CP CML, one patient in the group treated with BOSULIF experienced a Grade 3 QTcF prolongation (>500 msec). Patients with uncontrolled or significant cardiovascular disease including QT interval prolongation were excluded by protocol.

Table 8 identifies the clinically relevant or severe Grade 3/4 laboratory test abnormalities for the Phase 3 newly-diagnosed CML safety population.

Table 8: Select Laboratory Abnormalities (>20%) That Worsened From Baseline in Patients with Newly-Diagnosed CML in Bosutinib 400 mg Study [Based on a Minimum of 57 Months of Follow-up.]
 | Bosutinib N=268 % |  | Imatinib N=265 %
 | All Grade | Grade 3–4 | All Grade | Grade 3–4
Hematology Parameters
Platelet Count decreased | 68 | 14 | 60 | 6
Absolute Neutrophil Count decreased | 42 | 9 | 65 | 20
Hemoglobin decreased | 89 | 9 | 90 | 7
White Blood Cell Count decreased | 50 | 6 | 70 | 8
Lymphocyte Count decreased | 84 | 12 | 82 | 14
Biochemistry Parameters
SGPT/ALT increased | 68 | 26 | 28 | 3
SGOT/AST increased | 56 | 13 | 29 | 3.4
Lipase increased | 53 | 19 | 35 | 8
Phosphorus decreased | 54 | 9 | 69 | 21
Amylase increased | 32 | 3.4 | 18 | 2.3
Alkaline Phosphatase increased | 41 | 0 | 43 | 0.4
Calcium decreased | 55 | 1.5 | 57 | 1.1
Glucose increased | 57 | 3 | 65 | 3.4
Creatine Kinase increased | 36 | 3 | 65 | 5
Creatinine increased | 94 | 1.1 | 98 | 0.8
Abbreviations: ALT=alanine aminotransferase; AST=aspartate aminotransferase; CML=chronic myelogenous leukemia; SGPT=serum glutamic-pyruvic transaminase; SGOT=serum glutamic-oxaloacetic transaminase; N/n=number of patients; ULN=upper limit of normal.
Graded using CTCAE v 4.03

Adverse Reactions in Adult Patients With Imatinib-Resistant or -Intolerant Ph+ CP, AP, and BP CML

The single-arm clinical trial enrolled patients with Ph+ CP, AP, or BP CML and with resistance or intolerance to prior therapy [see Clinical Studies (14.2)]. The safety population (received at least 1 dose of BOSULIF) included 546 CML patients:

- two hundred eighty-four (284) patients with CP CML previously treated with imatinib only who had a median duration of BOSULIF treatment of 26 months (range: 0.2 to 155 months), and a median dose intensity of 437 mg/day.
- one hundred nineteen (119) patients with CP CML previously treated with both imatinib and at least 1 additional tyrosine kinase inhibitor (TKI) who had a median duration of BOSULIF treatment of 9 months (range: 0.2 to 148 months) and a median dose intensity of 427 mg/day.
- one hundred forty-three (143) patients with advanced phase (AdvP) CML including 79 patients with AP CML and 64 patients with BP CML. In the patients with AP CML and BP CML, the median duration of BOSULIF treatment was 10 months (range: 0.1 to 140 months) and 3 months (range: 0.03 to 71 months), respectively. The median dose intensity was 406 mg/day, and 456 mg/day, in the AP CML and BP CML cohorts, respectively.

Serious adverse reactions occurred in 30% of patients in the safety population of the single-arm trial in patients with CML (N=546) who were resistant or intolerant to prior therapy. Serious adverse reactions reported in >2% of patients included pneumonia (7%), pleural effusion (6%), pyrexia (3.7%), coronary artery disease (3.5%), dyspnea (2.6%), rash (2.2%), thrombocytopenia (2%), abdominal pain (2%), and diarrhea (2%).

Fatal adverse reactions occurred in 12 patients (2.2%) due to coronary artery disease (0.9%), pneumonia (0.4%), respiratory failure (0.4%), gastrointestinal hemorrhage (0.2%), acute kidney injury (0.2%), and acute pulmonary edema (0.2%).

Permanent discontinuation of bosutinib due to an adverse reaction occurred in 22% of patients with CML who were resistant or intolerant to prior therapy. Adverse reactions which resulted in permanent discontinuation in >2% of patients included thrombocytopenia (6%), hepatic dysfunction (3.3%), and neutropenia (2%).

Dose modifications (dose interruption or reductions) of bosutinib due to an adverse reaction occurred in 66% of patients with CML who were resistant or intolerant to prior therapy. Adverse reactions which required dose interruptions or reductions in >5% of patients included thrombocytopenia (24%), diarrhea (14%), rash (13%), hepatic dysfunction (10%), neutropenia (9%), pleural effusion (8%), vomiting (7%), anemia (6%), and abdominal pain (6%).

The most common adverse reactions, in ≥20% of patients in the safety population of the single-arm trial in patients with CML (N=546) who were resistant or intolerant to prior therapy were diarrhea (83%), nausea (47%), rash (46%), abdominal pain (45%), vomiting (39%), fatigue (33%), pyrexia (28%), hepatic dysfunction (27%), respiratory tract infection (24%), cough (23%), and headache (21%).

The most common laboratory abnormalities that worsened from baseline in ≥20% were creatinine increased (93%), hemoglobin decreased (91%), lymphocyte decreased (80%), platelets decreased (69%), absolute neutrophil count (54%), ALT increased (53%), calcium decreased (53%), white blood cell count decreased (52%), urate increased (48%), AST increased (47%), phosphorus decreased (39%), alkaline phosphatase increased (39%), lipase increased (28%), magnesium increased (25%), potassium decreased (24%), potassium increased (23%). See Table 10 for Grade 3/4 laboratory abnormalities.

Table 9 identifies adverse reactions greater than or equal to 10% for All Grades and Grades 3 or 4 for the Phase 1/2 CML safety population based on long-term follow-up.

Table 9: Adverse Reactions (10% or Greater) in Patients With CML Who Were Resistant or Intolerant to Prior Therapy in Single-Arm Trial [Based on a Minimum of 105 Months of Follow-up. Adverse drug reactions are based on all-causality treatment-emergent adverse events. The commonality stratification is based on 'All Grades' under Total column. 'Grade 3', 'Grade 4' columns indicate maximum toxicity]
 |  | CP CML (N=403) |  | AdvP CML (N=143)
System Organ Class | Preferred Term | All Grades % | Grade 3/4 % | All Grades % | Grade 3/4 %
Gastrointestinal disorders | Diarrhea | 85 | 10 | 76 | 4
 | Abdominal pain [Abdominal pain includes the following preferred terms: Abdominal discomfort, Abdominal pain, Abdominal pain lower, Abdominal pain upper, Abdominal tenderness, Dyspepsia, Epigastric discomfort, Gastrointestinal pain, Hepatic pain.] | 49 | 2 | 36 | 7
 | Nausea | 47 | 1 | 48 | 2
 | Vomiting | 38 | 3 | 43 | 3
 | Constipation | 15 | <1 | 17 | 1
Skin and subcutaneous tissue disorders | Rash [Rash includes the following preferred terms: Acarodermatitis, Acne, Angular cheilitis, Blister, Dermatitis, Dermatitis acneiform, Dermatitis psoriasiform, Drug eruption, Eczema, Eczema asteatotic, Erythema, Erythema annulare, Exfoliative rash, Lichenoid keratosis, Palmar erythema, Photosensitivity reaction, Pigmentation disorder, Psoriasis, Pyoderma gangrenosum, Pyogenic granuloma, Rash, Rash erythematous, Rash generalised, Rash macular, Rash maculo-papular, Rash pruritic, Rash pustular, Seborrhoeic dermatitis, Seborrhoeic keratosis, Skin depigmentation, Skin discoloration, Skin disorder, Skin exfoliation, Skin hyperpigmentation, Skin hypopigmentation, Skin irritation, Skin lesion, Skin plaque, Skin toxicity, Stasis dermatitis.] | 48 | 9 | 42 | 5
 | Pruritus | 12 | 1 | 7 | 0
General disorders and administration-site conditions | Fatigue | 35 | 3 | 27 | 6
 | Pyrexia | 25 | 1 | 37 | 3
 | Edema [Edema includes the following preferred terms: Eye edema, Eyelid edema, Face edema, Generalized edema, Localized edema, Edema, Edema peripheral, Penile edema, Periorbital edema, Periorbital swelling, Peripheral swelling, Scrotal edema, Scrotal swelling, Swelling, Swelling face, Swelling of eyelid, Testicular edema, Tongue edema.] | 19 | <1 | 17 | 1
 | Chest pain [Chest pain includes the following preferred terms: Chest discomfort, Chest pain.] | 8 | 1 | 12 | 1
Hepatobiliary disorders | Hepatic dysfunction [Hepatic dysfunction includes the following preferred terms: Alanine aminotransferase increased, Aspartate aminotransferase increased, Bilirubin conjugated increased, Blood alkaline phosphatase increased, Blood bilirubin increased, Blood bilirubin unconjugated increased, Gamma-glutamyltransferase increased, Hepatic enzyme increased, Hepatic function abnormal, Hepatic steatosis, Hepatitis toxic, Hepatomegaly, Hepatotoxicity, Hyperbilirubinemia, Liver disorder, Liver function test abnormal, Liver function test increased, Transaminases increased.] | 29 | 11 | 21 | 10
Infections and infestations | Respiratory tract infection [Respiratory tract infection includes the following preferred terms: Nasopharyngitis, Respiratory tract congestion, Respiratory tract infection, Respiratory tract infection viral, Upper respiratory tract infection, Viral upper respiratory tract infection.] | 27 | <1 | 17 | 0
 | Influenza [Influenza includes the following preferred terms: H1N1 influenza, Influenza.] | 11 | 1 | 3 | 0
 | Pneumonia [Pneumonia includes the following preferred terms: Atypical pneumonia, Lower respiratory tract congestion, Lower respiratory tract infection, Pneumonia, Pneumonia aspiration, Pneumonia bacterial, Pneumonia fungal, Pneumonia necrotising, Pneumonia streptococcal.] | 10 | 4 | 18 | 12
Respiratory, thoracic, and mediastinal disorders | Cough | 24 | 0 | 22 | 0
 | Pleural effusion | 14 | 4 | 9 | 4
 | Dyspnea | 12 | 2 | 20 | 6
Nervous system disorders | Headache | 21 | 1 | 18 | 4
 | Dizziness | 11 | 0 | 14 | 1
Musculoskeletal and connective tissue disorders | Arthralgia | 19 | 1 | 15 | 0
 | Back pain | 14 | 1 | 8 | 1
Metabolism and nutrition disorders | Decreased appetite | 14 | 1 | 14 | 0
Vascular disorders | Hypertension [Hypertension* includes the following preferred terms: Blood pressure increased, Blood pressure systolic increased, Essential hypertension, Hypertension, Hypertensive crisis, Retinopathy hypertensive. * ADR identified post-marketing] | 11 | 3 | 8 | 3
ADR Definition

In the single-arm study in patients with CML who were resistant or intolerant to prior therapy, 2 patients (0.4%) experienced QTcF interval of greater than 500 milliseconds. Patients with uncontrolled or significant cardiovascular disease including QT interval prolongation were excluded by protocol.

Table 10 identifies the clinically relevant or severe Grade 3/4 laboratory test abnormalities for the safety population of the study in patients with CML who were resistant or intolerant to prior therapy based on long-term follow-up.

Table 10: Number (%) of Patients With Clinically Relevant All Grade or Grade 3/4 Laboratory Test Abnormalities in the Safety Population of the Study of Patients With CML Who Were Resistant or Intolerant to Prior Therapy [Based on a Minimum of 105 Months of Follow-up.]
 | CP CML N=403 % |  | AdvP CML N=143 %
 | All grade | Grade 3/4 | All grade | Grade 3/4
Hematology Parameters
Platelet Count decreased | 66 | 26 | 80 | 57
Absolute Neutrophil Count decreased | 50 | 16 | 66 | 39
Hemoglobin decreased | 89 | 13 | 97 | 38
Lymphocyte decreased | 79 | 14 | 82 | 21
White Blood Cell Count decreased | 51 | 7 | 57 | 27
Biochemistry Parameters
SGPT/ALT increased | 58 | 11 | 39 | 6
SGOT/AST increased | 50 | 5 | 37 | 3.5
Lipase increased | 32 | 12 | 19 | 6
Phosphorus decreased | 41 | 8 | 33 | 7
Total Bilirubin increased | 16 | 0.7 | 22 | 2.8
Creatinine increased | 95 | 3 | 87 | 1.4
Alkaline Phosphatase increased | 39 | 0 | 39 | 1.4
Glucose increased | 42 | 2.7 | 39 | 6
Sodium increased | 23 | 0.5 | 11 | 0
Sodium decreased | 18 | 2.2 | 27 | 6
Calcium decreased | 55 | 4.7 | 45 | 3.5
Urate increased | 49 | 6 | 43 | 6
Magnesium increased | 27 | 7 | 18 | 4.9
Potassium decreased | 22 | 1.7 | 29 | 4.9
Potassium increased | 25 | 2.7 | 19 | 2.1
Abbreviations: AdvP=advanced phase; ALT=alanine aminotransferase; AST=aspartate aminotransferase; CML=chronic myelogenous leukemia; CP=chronic phase; N/n=number of patients; SGPT=serum glutamate-pyruvate transaminase; SGOT=serum glutamate-oxaloacetate aminotransferase; ULN=upper limit of normal.

Pediatric Patients with Newly-Diagnosed CP Ph+ CML or CP Ph+ CML that is Resistant or Intolerant to Prior Therapy

The safety of BOSULIF was evaluated in BCHILD, a single-arm trial for the treatment of pediatric patients aged 1 year and older with newly-diagnosed CP Ph+ CML or in patients with CP Ph+ CML who are resistant or intolerant to prior therapy [see Clinical Studies (14.3)]. Patients received BOSULIF (n = 49) 300 mg/m^2 to 400 mg/m^2 orally once daily until disease progression or unacceptable toxicity. The median time on treatment with BOSULIF was 12.2 months (range, 0.2 to 60.9 months). Among patients who received BOSULIF, 77.6% were exposed for 6 months or longer and 51% were exposed for one year or longer.

Permanent discontinuation of BOSULIF due to an adverse reaction occurred in 20% of patients. Adverse reactions which resulted in permanent discontinuation in 2 or more patients included ALT increased (6%), AST increased (4%), diarrhea (4%), fatigue (4%) and rash maculo-papular (4%).

The most common adverse reactions, in ≥20% of BOSULIF-treated pediatric patients were diarrhea, abdominal pain, vomiting, nausea, rash, fatigue, hepatic dysfunction, headache, pyrexia, decreased appetite, and constipation.

Table 11 summarizes the adverse reactions in BCHILD.

Table 11: Adverse Reactions (10% or Greater) in Pediatric Patients with Newly Diagnosed CP Ph+ CML or CP Ph+ CML Resistant or Intolerant to Prior Therapy Who Received BOSULIF in BCHILD
System Organ Class | Preferred Term | BOSULIF Total (N=49); %
System Organ Class | Preferred Term | All Grades | Grade 3/4
Gastrointestinal disorders | Diarrhea | 82 | 12
 | Abdominal pain [Abdominal pain includes the following preferred terms: Abdominal discomfort, Abdominal pain, Abdominal pain lower, Abdominal pain upper, Abdominal tenderness, Dyspepsia, Epigastric discomfort, Gastrointestinal pain, Hepatic pain.] | 73 | 4
 | Vomiting | 55 | 6
 | Nausea | 49 | 2
 | Constipation | 20 | 0
Skin and subcutaneous tissue disorders | Rash [Rash includes the following preferred terms: Acarodermatitis, Acne, Angular cheilitis, Blister, Dermatitis, Dermatitis acneiform, Dermatitis bullous, Dermatitis exfoliative generalized, Dermatitis psoriasiform, Drug eruption, Drug reaction with eosinophilia and systemic symptoms, Dyshidrotic eczema, Eczema, Eczema asteatotic, Erythema, Erythema annulare, Erythema nodosum, Exfoliative rash, Genital rash, Lichen planus, Lichenoid keratosis, Palmar erythema, Palmar-plantar erythrodysesthesia syndrome, Perivascular dermatitis, Photosensitivity reaction, Pigmentation disorder, Pruritus allergic, Psoriasis, Punctate keratitis, Pyoderma gangrenosum, Pyogenic granuloma, Rash, Rash erythematous, Rash generalized, Rash macular, Rash maculo-papular, Rash papular, Rash pruritic, Rash pustular, Rash vesicular, Seborrheic dermatitis, Seborrhoeic keratosis, Skin depigmentation, Skin discoloration, Skin disorder, Skin exfoliation, Skin hyperpigmentation, Skin hypopigmentation, Skin irritation, Skin lesion, Skin plaque, Skin reaction, Skin toxicity, Stasis dermatitis.] | 49 | 8
Hepatobiliary disorders | Hepatic dysfunction [Hepatic dysfunction includes the following preferred terms: Alanine aminotransferase abnormal, Alanine aminotransferase increased, Aspartate aminotransferase, Aspartate aminotransferase increased, Bilirubin conjugated increased, Blood alkaline phosphatase increased, Blood bilirubin increased, Blood bilirubin unconjugated increased, Gamma-glutamyltransferase increased, Hepatic enzyme increased, Hepatomegaly, Hepatosplenomegaly, Hyperbilirubinaemia, Jaundice, Liver function test abnormal, Liver function test increased, Ocular icterus, Transaminases increased, Hepatic function abnormal, Drug-induced liver injury, Hepatic steatosis, Hepatitis, Hepatitis toxic, Hepatobiliary disease, Hepatocellular injury, Hepatotoxicity, Liver disorder, Liver injury.] | 37 | 14
General disorders and administration-site conditions | Fatigue [Fatigue includes the following preferred terms: Asthenia, Fatigue, Malaise.] | 37 | 4
 | Pyrexia | 31 | 4
Nervous system disorders | Headache | 35 | 2
Metabolism and nutrition disorders | Decreased appetite | 27 | 2
Infections and infestations | Respiratory tract infection [Respiratory tract infection includes the following preferred terms: Nasopharyngitis, Respiratory tract congestion, Respiratory tract infection, Respiratory tract infection viral, Upper respiratory tract congestion, Upper respiratory tract infection, Upper respiratory tract inflammation, Viral upper respiratory tract infection.] | 12 | 2
Adverse drug reactions are based on all-causality treatment-emergent adverse reactions.
The commonality stratification is based on 'All Grades' under Bosutinib 400 mg column.
'Grade 3/4 columns indicate maximum toxicity.

The most common laboratory abnormalities that worsened from baseline in ≥20% of patients were creatinine increased, alanine aminotransferase increased, white blood cell count decreased, aspartate aminotransferase increased, platelet count decreased, glucose increased, calcium decreased, hemoglobin decreased, neutrophil count decreased, lymphocyte count decreased, serum amylase increased and CPK increased.

Table 12 summarizes laboratory test abnormalities in BCHILD.

Table 12: Laboratory Abnormalities (≥ 20%) That Worsened From Baseline in Pediatric Patients with Newly-Diagnosed CP Ph+ CML or CP Ph+ CML Resistant or Intolerant to Prior Therapy Who Received BOSULIF in BCHILD
 | BOSULIF (N= 49)
 | All Grade | Grade 3/4
 | % | %
Creatinine increased | 92 | 0
Alanine aminotransferase increased | 59 | 14
White blood cell count decreased | 53 | 4
Aspartate aminotransferase increased | 51 | 6
Platelet count decreased | 49 | 18
Glucose increased | 41 | 0
Calcium decreased | 31 | 0
Hemoglobin decreased | 31 | 8
Neutrophil count decreased | 31 | 12
Lymphocyte count decreased | 29 | 2
Serum amylase increased | 27 | 4
CPK increased | 25 | 0
Grades are defined using CTCAE V4.03. Based on CTCAE grading without regard to fasting status for 'Hyperglycemia' lab parameter.
Includes data up to 28 days after last dose of study treatment.

Additional Adverse Reactions From Multiple Clinical Trials

The following adverse reactions were reported in patients in clinical trials with BOSULIF (less than 10% of BOSULIF-treated patients). They represent an evaluation of the adverse reaction data from all 1372 patients with leukemia who received at least 1 dose of single-agent BOSULIF. These adverse reactions are presented by system organ class and are ranked by frequency. These adverse reactions are included based on clinical relevance and ranked in order of decreasing seriousness within each category.

Blood and Lymphatic System Disorders: 0.1% and less than 1% - Febrile neutropenia

Cardiac Disorders: 1% and less than 10% - Cardiac ischemia (includes Acute coronary syndrome, Acute myocardial infarction, Angina pectoris, Angina unstable, Arteriosclerosis coronary artery, Coronary artery disease, Coronary artery occlusion, Coronary artery stenosis, Myocardial infarction, Myocardial ischemia, Troponin increased), Pericardial effusion, Cardiac failure (includes Cardiac failure, Cardiac failure acute, Cardiac failure chronic, Cardiac failure congestive, Cardiogenic shock, Cardiorenal syndrome, Ejection fraction decreased, Left ventricular failure); 0.1% and less than 1% - Pericarditis

Ear and Labyrinth Disorders: 1% and less than 10% - Tinnitus

Endocrine Disorders: 1% and less than 10% - Hypothyroidism; 0.1% and less than 1% - Hyperthyroidism

Gastrointestinal Disorders: 1% and less than 10% - Gastritis, Pancreatitis (includes Edematous pancreatitis, Pancreatic enzymes increased, Pancreatitis, Pancreatitis acute, Pancreatitis chronic), Gastrointestinal hemorrhage (includes Anal hemorrhage, Gastric hemorrhage, Gastrointestinal hemorrhage, Intestinal hemorrhage, Lower gastrointestinal hemorrhage, Rectal hemorrhage, Upper gastrointestinal hemorrhage)

General Disorders and Administrative Site Conditions: 1% and less than 10% - Pain

Immune System Disorders: 1% and less than 10% - Drug hypersensitivity; 0.1% and less than 1% - Anaphylactic shock

Infections and Infestations: 1% and less than 10% - Bronchitis

Investigations: 1% and less than 10% - Electrocardiogram QT prolonged (includes Electrocardiogram QT prolonged, Long QT syndrome)

Metabolism and Nutrition Disorders: 1% and less than 10% - Dehydration

Musculoskeletal and Connective Tissue Disorders: 1% and less than 10% - Myalgia

Nervous System Disorders: 1% and less than 10% - Dysgeusia

Renal and Urinary Disorders: 1% and less than 10% - Acute kidney injury, Renal impairment, Renal failure

Respiratory, Thoracic and Mediastinal Disorders: 1% and less than 10% - Pulmonary hypertension (includes Pulmonary hypertension, Pulmonary arterial hypertension, Pulmonary arterial pressure increased); 0.1% and less than 1% - Acute pulmonary edema (includes Acute pulmonary edema, Pulmonary edema), Interstitial lung disease, Respiratory failure

Skin and Subcutaneous Disorders: 0.1% and less than 1% - Erythema multiforme

6.2 Postmarketing Experience

The following additional adverse reactions have been identified during post-approval use of BOSULIF. Because these reactions are reported voluntarily from a population of uncertain size, it is not always possible to reliably estimate their frequency or establish a causal relationship to drug exposure.

Blood and Lymphatic System Disorders: Thrombotic microangiopathy

Skin and Subcutaneous Tissue Disorders: Stevens-Johnson syndrome

7 DRUG INTERACTIONS

7.1 Effect of Other Drugs on BOSULIF

Strong or Moderate CYP3A Inhibitors

Avoid the concomitant use of strong or moderate CYP3A inhibitors with BOSULIF. Bosutinib is a CYP3A substrate. Concomitant use with a strong or moderate CYP3A inhibitor increases bosutinib Cmax and AUC [see Clinical Pharmacology (12.3)] which may increase the risk of toxicities.

Strong CYP3A Inducers

Avoid the concomitant use of strong CYP3A inducers with BOSULIF. Bosutinib is a CYP3A substrate. Concomitant use with a strong CYP3A inducer decreases bosutinib Cmax and AUC [see Clinical Pharmacology (12.3)] which may reduce BOSULIF efficacy.

Proton Pump Inhibitors (PPI)

As an alternative to PPIs, use short-acting antacids or H2 blockers and separate dosing by more than 2 hours from BOSULIF dosing. Bosutinib displays pH dependent aqueous solubility, Concomitant use with a PPI decreases bosutinib Cmax and AUC [see Clinical Pharmacology (12.3)] which may reduce BOSULIF efficacy.

8 USE IN SPECIFIC POPULATIONS

8.1 Pregnancy

Risk Summary

Based on findings from animal studies and its mechanism of action, BOSULIF can cause fetal harm when administered to a pregnant woman [see Clinical Pharmacology (12.1)].

There are no available data in pregnant women to inform the drug-associated risk. In animal reproduction studies conducted in rats and rabbits, oral administration of bosutinib during organogenesis caused adverse developmental outcomes, including structural abnormalities, embryo-fetal mortality, and alterations to growth at maternal exposures (AUC) as low as 1.2 times the human exposure at the dose of 500 mg/day (see Data). Advise pregnant women of the potential risk to a fetus.

The background risk of major birth defects and miscarriage for the indicated population is unknown. All pregnancies have a background risk of birth defect, loss, or other adverse outcomes. In the U.S. general population, the estimated background risk of major birth defects and miscarriage in clinically recognized pregnancies are 2–4% and 15–20%, respectively.

Data

Animal Data

In a rat fertility and early embryonic development study, bosutinib was administered orally to female rats for approximately 3 to 6 weeks, depending on day of mating (2 weeks prior to cohabitation with untreated breeder males until gestation day [GD] 7). Increased embryonic resorptions occurred at greater than or equal to 10 mg/kg/day of bosutinib (1.6 and 1.2 times the human exposure at the recommended doses of 400 or 500 mg/day, respectively), and decreased implantations and reduced number of viable embryos at 30 mg/kg/day of bosutinib (3.4 and 2.5 times the human exposure at the recommended doses of 400 or 500 mg/day, respectively).

In an embryo-fetal development study conducted in rabbits, bosutinib was administered orally to pregnant animals during the period of organogenesis at doses of 3, 10, and 30 mg/kg/day. At the maternally-toxic dose of 30 mg/kg/day of bosutinib, there were fetal anomalies (fused sternebrae, and 2 fetuses had various visceral observations), and an approximate 6% decrease in fetal body weight. The dose of 30 mg/kg/day resulted in exposures (AUC) approximately 5.1 and 3.8 times the human exposures at the recommended doses of 400 and 500 mg/day, respectively.

Fetal exposure to bosutinib-derived radioactivity during pregnancy was demonstrated in a placental-transfer study in pregnant rats. In a rat pre- and postnatal development study, bosutinib was administered orally to pregnant animals during the period of organogenesis through lactation day 20 at doses of 10, 30, and 70 mg/kg/day. Reduced number of pups born occurred at greater than or equal to 30 mg/kg/day bosutinib (3.4 and 2.5 times the human exposure at the recommended doses of 400 or 500 mg/day, respectively), and increased incidence of total litter loss and decreased growth of offspring after birth occurred at 70 mg/kg/day bosutinib (6.9 and 5.1 times the human exposure at the recommended doses of 400 or 500 mg/day, respectively).

8.2 Lactation

Risk Summary

No data are available regarding the presence of bosutinib or its metabolites in human milk or its effects on a breastfed child or on milk production. However, bosutinib is present in the milk of lactating rats. Because of the potential for serious adverse reactions in a nursing child, breastfeeding is not recommended during treatment with BOSULIF and for 2 weeks after the last dose.

Animal Data

After a single radiolabeled bosutinib dose to lactating rats, radioactivity was present in the plasma of suckling offspring for 24 to 48 hours.

8.3 Females and Males of Reproductive Potential

Based on findings from animal studies, BOSULIF can cause fetal harm when administered to a pregnant woman [see Use in Specific Populations (8.1)].

Pregnancy

Females of reproductive potential should have a pregnancy test prior to starting treatment with BOSULIF.

Contraception

Females

Advise females of reproductive potential to use effective contraception (methods that result in less than 1% pregnancy rates) during treatment with BOSULIF and for 2 weeks after the last dose.

Infertility

The risk of infertility in females or males of reproductive potential has not been studied in humans. Based on findings from animal studies, BOSULIF may cause reduced fertility in females and males of reproductive potential [see Nonclinical Toxicology (13.1)].

8.4 Pediatric Use

The safety and effectiveness of BOSULIF have been established in pediatric patients 1 year of age and older with newly-diagnosed CP Ph+ CML and CP Ph+ CML that is resistant or intolerant to prior therapy.

Use of BOSULIF for these indications is based on data from BCHILD [NCT04258943]. The study included pediatric patients with newly diagnosed CP Ph+ CML in the following age groups: 2 patients 1 year of age to less than 6 years of age, 3 patients 6 years of age to less than 12 years of age, and 10 patients 12 years of age to less than 17 years of age. The study also included pediatric patients with CP Ph+ CML that was resistant or intolerant to prior therapy in the following age groups: 4 patients 1 year of age to less than 6 years of age, 10 patients 6 years of age to less than 12 years of age, and 10 patients 12 years of age to less than 17 years of age [see Adverse Reactions (6.1) and Clinical Studies (14.3)]. BSA-normalized apparent clearance in 27 pediatric patients aged 4 to <17 years (141.3 L/h/m^2) was 29% higher than BSA-normalized apparent clearance in adult patients with CP Ph+ CML (109.2 L/h/m^2) [see Clinical Pharmacology (12.3)]. The recommended dosage of BOSULIF in pediatric patients is based on body surface area (BSA) [see Dosage and Administration (2.1)].

The safety and effectiveness of BOSULIF in pediatric patients younger than 1 year of age with newly diagnosed CP Ph+ CML, pediatric patients younger than 1 year of age with CP Ph+ CML that is resistant or intolerant to prior therapy, and pediatric patients with AP Ph+ CML or BP Ph+ CML have not been established.

8.5 Geriatric Use

In the single-arm study in patients with CML who were resistant or intolerant to prior therapy of BOSULIF in patients with Ph+ CML, 20% were age 65 and over, 4% were 75 and over. Of the 268 patients who received bosutinib in the study for newly diagnosed CML, 20% were age 65 and over, 5% were 75 and over. No overall differences in safety or effectiveness were observed between these patients and younger patients, and other reported clinical experience has not identified differences in responses between the elderly and younger patients, but greater sensitivity of some older individuals cannot be ruled out.

8.6 Renal Impairment

Reduce the BOSULIF starting dose in patients with moderate (creatinine clearance [CLcr] 30 to 50 mL/min, estimated by Cockcroft-Gault (C-G)) and severe (CLcr less than 30 mL/min, C-G) renal impairment at baseline. For patients who have declining renal function while on BOSULIF who cannot tolerate the starting dose, follow dose adjustment recommendations for toxicity [see Dosage and Administration (2.3, 2.5) and Clinical Pharmacology (12.3)]. BOSULIF has not been studied in patients undergoing hemodialysis.

8.7 Hepatic Impairment

Reduce the BOSULIF dosage in patients with hepatic impairment (Child-Pugh A, B, or C) [see Dosage and Administration (2.3, 2.5) and Clinical Pharmacology (12.3)].

10 OVERDOSAGE

Experience with BOSULIF overdose in clinical studies was limited to isolated cases. There were no reports of any serious adverse events associated with the overdoses. Patients who take an overdose of BOSULIF should be observed and given appropriate supportive treatment.

11 DESCRIPTION

BOSULIF contains bosutinib, a kinase inhibitor. Bosutinib is present as a monohydrate with a chemical name of 3-Quinolinecarbonitrile, 4-[(2,4-dichloro-5-methoxyphenyl)amino]-6-methoxy-7-[3-(4-methyl-1-piperazinyl) propoxy]-, hydrate (1:1). Its chemical formula is C26H29Cl2N5O3∙H2O (monohydrate); its molecular weight is 548.46 (monohydrate), equivalent to 530.46 (anhydrous). Bosutinib monohydrate has the following chemical structure:

Bosutinib monohydrate is a white to yellowish-tan powder. Bosutinib monohydrate has a pH dependent solubility across the physiological pH range. At or below pH 5, bosutinib monohydrate behaves as a highly soluble compound. Above pH 5, the solubility of bosutinib monohydrate reduces rapidly.

BOSULIF® (bosutinib) tablets are supplied for oral administration in 3 strengths: 100 mg, 400 mg and 500 mg. Each strength reflects the equivalent amount of bosutinib content (on anhydrous basis). The tablets contain the following inactive ingredients: croscarmellose sodium, iron oxide red (for 400 mg, and 500 mg tablet) and iron oxide yellow (for 100 mg, and 400 mg tablet), magnesium stearate, microcrystalline cellulose, poloxamer, polyethylene glycol, polyvinyl alcohol, povidone, talc and titanium dioxide.

BOSULIF® (bosutinib) capsules are supplied for oral administration in 2 strengths: 50 mg and 100 mg. Each strength reflects the equivalent amount of bosutinib (on anhydrous basis). The capsules contain the following inactive ingredients: croscarmellose sodium, gelatin, magnesium stearate, mannitol, microcrystalline cellulose, poloxamer, povidone, red iron oxide, titanium dioxide, yellow iron oxide. The printing ink contains black iron oxide, potassium hydroxide, propylene glycol, shellac, strong ammonia solution.

12 CLINICAL PHARMACOLOGY

12.1 Mechanism of Action

Bosutinib is a TKI. Bosutinib inhibits the BCR-ABL kinase that promotes CML; it is also an inhibitor of Src-family kinases including Src, Lyn, and Hck. Bosutinib inhibited 16 of 18 imatinib-resistant forms of BCR-ABL kinase expressed in murine myeloid cell lines. Bosutinib did not inhibit the T315I and V299L mutant cells.

12.2 Pharmacodynamics

A greater likelihood of response and a greater likelihood of safety events were observed with higher bosutinib exposure in clinical studies. The time course of bosutinib pharmacodynamic response has not been fully characterized.

Cardiac Electrophysiology

At a single oral dose of 500 mg BOSULIF with ketoconazole (a strong CYP3A inhibitor), BOSULIF does not prolong the QT interval to any clinically relevant extent.

12.3 Pharmacokinetics

Bosutinib pharmacokinetics were assessed following oral dosing with food in adult patients with CML and were presented as geometric mean (CV%), unless otherwise specified.

Bosutinib exhibits dose proportional increases in Cmax and AUC over the oral dose range of 200 to 800 mg (0.33 to 1.3 times the maximum approved recommended dosage of 600 mg). Bosutinib steady state Cmax was 127 ng/mL (31%), Ctrough was 68 ng/mL (39%) and AUC was 2370 ng•h/mL (34%) following multiple oral doses of BOSULIF 400 mg; Bosutinib steady state Cmax was 171 ng/mL (38%), Ctrough was 91 ng/mL (42%) and AUC was 3150 ng•h/mL (38%) following multiple oral doses of BOSULIF 500 mg. No clinically significant differences in the pharmacokinetics of bosutinib were observed following administration of either the tablet or capsule dosage forms of BOSULIF at the same dose, under fed conditions.

Absorption

The median bosutinib (minimum, maximum) time-‑to-Cmax (tmax) was 6.0 (6.0, 6.0) hours following oral administration of a single oral dose of BOSULIF 500 mg with food. The absolute bioavailability was 34% in healthy subjects.

Effect of Food

Bosutinib Cmax increased 1.8-fold and AUC increased 1.7-fold when BOSULIF tablets were given with a high fat meal to healthy subjects compared to administration under fasted condition. Bosutinib Cmax increased 1.6‑fold and AUC increased 1.5-fold when BOSULIF capsules were given with a high fat meal to healthy subjects compared to administration under fasted condition. The high-fat meal (800-1000 total calories) consisted of approximately 150 protein calories, 250 carbohydrate calories, and 500-600 fat calories.

No clinically significant differences in the pharmacokinetics of bosutinib were observed following administration of a BOSULIF capsule that was opened and the contents mixed with applesauce or yogurt immediately before use.

Distribution

The mean (SD) apparent bosutinib volume of distribution is 6080 (1230) L after an oral dose of 500 mg of BOSULIF.

Bosutinib protein binding is 94% in vitro and 96% ex vivo, and is independent of concentration.

Elimination

The mean (SD) bosutinib terminal phase elimination half life (t½) was 22.5 (1.7) hours, and the mean (SD) apparent clearance was 189 (48) L/h following a single oral dose of BOSULIF.

Metabolism

Bosutinib is primarily metabolized by CYP3A4.

Excretion

Following a single oral dose of [^14C] radiolabeled bosutinib without food, 91.3% of the dose was recovered in feces and 3.3% of the dose recovered in urine.

Specific Populations

Patients with Renal Impairment

Bosutinib AUC increased 1.4-fold in subjects with moderate renal impairment (CLcr: 30 to 50 mL/min, estimated by Cockcroft-Gault (C-G)) and increased 1.6-fold in subjects with severe renal impairment (CLcr less than 30 mL/min) following a single oral dose of BOSULIF 200 mg (0.33 times the maximum approved recommended dosage of 600 mg). No clinically significant difference in the pharmacokinetics of bosutinib was observed in subjects with mild renal impairment (CLcr: 51 to 80 mL/min, C-G). BOSULIF has not been studied in patients undergoing hemodialysis.

Patients with Hepatic Impairment

Bosutinib Cmax increased 2.4-fold, 2-fold, and 1.5-fold, and AUC increased 2.3-fold, 2-fold, and 1.9-fold in hepatic impairment Child-Pugh A, B, and C, respectively, following a single oral dose of BOSULIF 200 mg (0.33 times the maximum approved recommended dosage of 600 mg).

Pediatric Patients

The pharmacokinetics of bosutinib in 27 pediatric patients aged 4 to less than 17 years with newly diagnosed CP Ph+ CML or resistant/intolerant CP Ph+ CML were evaluated over the dose range of 300 mg/m^2 to 400 mg/m^2 administered orally once daily with food. Exposures increased in a dose proportional manner over the dose range of 300 mg/m^2 to 400 mg/m^2. The bosutinib median (min, max) tmax is approximately 3 hours post-dose (1, 8 hours). In 15 pediatric patients aged 4 to less than 17 years who received 300 mg/m^2 daily, steady state Cmax was 159 ng/mL (42%), Ctrough was 49 ng/mL (53%) and AUC was 2027 ng•h/mL (47%). In 6 pediatric patients aged 6 to less than 17 years who received 400 mg/m^2 daily, steady state Cmax was 198 ng/mL (37%), Ctrough was 42 ng/mL (105%), and AUC was 2514 ng•h/mL (35%).

An increase in BSA correlated with an increase in apparent clearance and exposure metrics did not significantly differ across BSA or age in pediatric patients following the approved recommended BSA-based dosage.

Drug Interaction Studies

Clinical Studies

Strong CYP3A Inhibitors: Bosutinib Cmax increased 5.2-fold and AUC increased 8.6-foldfollowing a single dose of BOSULIF 100 mg (0.17 times the maximum approved recommended dosage) without food when used concomitantly with 400 mg ketoconazole (a strong CYP3A inhibitor) administered over multiple daily doses.

Moderate CYP3A Inhibitors: Bosutinib Cmax increased 1.5-fold and AUC increased 2.0-fold following a single dose of BOSULIF 500 mg with food when administered concomitantly with 125 mg aprepitant (a moderate CYP3A inhibitor).

Strong CYP3A Inducers: Bosutinib Cmax decreased by 86% and AUC decreased by 94% following a single dose of BOSULIF 500 mg with food administered concomitantly with multiple daily doses of 600 mg of rifampin (a strong CYP3A inducer).

Proton Pump Inhibitors: Lansoprazole decreased bosutinib Cmax by 46% and AUC by 26% following a single oral dose of BOSULIF 400 mg without food when used concomitantly with lansoprazole 60 mg (proton pump inhibitor) administered over multiple daily doses. Bosutinib displays pH‑dependent aqueous solubility, in vitro [see Description (11)].

P-gp Substrates: No clinically significant differences in bosutinib pharmacokinetics were observed when used concomitantly with dabigatran etexilate mesylate (a P-glycoprotein (P-gp) substrate).

In Vitro Studies

Transporters Systems:

Bosutinib inhibits breast cancer resistance protein (BCRP)but, does not inhibit organic anion transporting polypeptide (OATP)1B1, OATP1B3, organic anion transporter (OAT)1, OAT3, organic cation transporter (OCT)1, and OCT2.

13 NONCLINICAL TOXICOLOGY

13.1 Carcinogenesis, Mutagenesis, Impairment of Fertility

Bosutinib was not carcinogenic in rats or transgenic mice. The rat 2-year carcinogenicity study was conducted at bosutinib oral doses up to 25 mg/kg in males and 15 mg/kg in females. Exposures at these doses were approximately 1.5 times (males) and 3.1 times (females) the human exposure at the 400 mg dose and 1.2 times (males) and 2.4 times (females) exposure in humans at the 500 mg dose. The 6-month RasH2 transgenic mouse carcinogenicity study was conducted at bosutinib oral doses up to 60 mg/kg.

Bosutinib was not mutagenic or clastogenic in a battery of tests, including the bacteria reverse mutation assay (Ames Test), the in vitro assay using human peripheral blood lymphocytes and the micronucleus test in orally treated male mice.

In a rat fertility study, drug-treated males were mated with untreated females, or untreated males were mated with drug-treated females. Females were administered the drug from pre-mating through early embryonic development. The dose of 70 mg/kg/day of bosutinib resulted in reduced fertility in males as demonstrated by 16% reduction in the number of pregnancies. There were no lesions in the male reproductive organs at this dose. This dose of 70 mg/kg/day resulted in exposure (AUC) in male rats approximately 1.5 times and equal to the human exposure at the recommended doses of 400 and 500 mg/day, respectively. Fertility (number of pregnancies) was not affected when female rats were treated with bosutinib. However, there were increased embryonic resorptions at greater than or equal to 10 mg/kg/day of bosutinib (1.6 and 1.2 times the human exposure at the recommended doses of 400 and 500 mg/day, respectively), and decreased implantations and reduced number of viable embryos at 30 mg/kg/day of bosutinib (3.4 and 2.5 times the human exposure at the recommended doses of 400 or 500 mg/day, respectively).

14 CLINICAL STUDIES

14.1 Adult Patients with Newly-Diagnosed CP Ph+ CML

The efficacy of BOSULIF in patients with newly-diagnosed chronic phase Ph+ CML was evaluated in the Bosutinib trial in First-line chrOnic myelogenous leukemia tREatment (BFORE) Trial: "A Multicenter Phase 3, Open-Label Study of Bosutinib Versus Imatinib in Adult Patients With Newly Diagnosed Chronic Phase Chronic Myelogenous Leukemia" [NCT02130557].

The BFORE Trial is a 2-arm, open-label, randomized, multicenter trial conducted to investigate the efficacy and safety of BOSULIF 400 mg once daily alone compared with imatinib 400 mg once daily alone in adult patients with newly-diagnosed CP Ph+ CML. The trial randomized 536 patients (268 in each arm) with Ph+ or Ph- newly-diagnosed CP CML (intent-to-treat [ITT] population) including 487 patients with Ph+ CML harboring b2a2 and/or b3a2 transcripts at baseline and baseline BCR-ABL copies >0 (modified intent-to-treat [mITT] population). Randomization was stratified by Sokal score and geographical region. All patients are being treated and/or followed for up to 5 years (240 weeks). Efficacy was evaluated in the mITT population. The major efficacy outcome measure was major molecular response (MMR) at 12 months (48 weeks) defined as ≤0.1% BCR-ABL ratio on international scale (corresponding to ≥3 log reduction from standardized baseline) with a minimum of 3000 ABL transcripts as assessed by the central laboratory. Additional efficacy outcomes included CCyR by 12 months, defined as the absence of Ph+ metaphases in chromosome banding analysis of ≥20 metaphases derived from bone marrow aspirate or MMR if an adequate cytogenetic assessment was unavailable and MMR by 18 months (72 weeks).

In the mITT population in this study, 57% of patients were males, 78% were Caucasian, and 19% were 65 years or older. The median age was 53 years. At baseline, the distribution of Sokal risk scores was similar in bosutinib and imatinib-treated patients (low risk: 35% and 39%; intermediate risk: 44% and 38%; high risk: 22% and 22%, respectively). After a minimum of 12 months follow-up, 78% of the 246 bosutinib-treated patients and 72% of the 239 imatinib-treated patients were still receiving treatment and with a minimum of 60 months of follow-up, 60% and 60% of patients, respectively, were still receiving treatment. The median treatment duration was 55.1 months for BOSULIF and 55.0 months for imatinib.

The efficacy results from the BFORE trial are summarized in Table 13.

Table 13: Summary of Major Molecular Response (MMR) and Complete Cytogenetic Response (CCyR), by Treatment Group in the Modified Intent-to-Treat (mITT) Population
Response | Bosutinib N=246 n (%) | Imatinib N=241 n (%) | 2-sided p-value
MMR at Month 12 (Week 48)
MMR (%) | 116 (47) | 89 (37) | 0.0200 [Derived from CMH test stratified by Geographical region and Sokal score at randomization.]
(95% CI) | (41, 53) | (31, 43)
CCyR by Month 12 (Week 48)
CCyR (%) | 190 (77) | 160 (66)
(95% CI) | (72, 83) | (60, 72) | 0.0075
MMR by Month 18 (Week 72)
MMR (%) | 150 (61) | 127 (53)
(95% CI) | (55, 67) | (46, 59) | 0.0606
Abbreviations: CCyR=complete cytogenetic response; CI=confidence interval; CMH=Cochran-Mantel-Haenszel; MMR=major molecular response; N/n=number of patients.

The MMR rate at Month 12 for all randomized patients (ITT population) was consistent with the mITT population (47% [95% CI: 41, 53] in the bosutinib treatment group and 36% [95% CI: 30, 42] in the imatinib treatment group; odds ratio of 1.57 [95% CI: 1.10, 2.22]). MMR by Month 60 (Week 240) in the mITT population was 74% (95% CI: 69, 80) in the bosutinib treatment group and 66% (95% CI: 60, 72) in the imatinib treatment group; odds ratio of 1.52 (95% CI: 1.02, 2.25). MMR by Month 60 in the ITT population was also consistent with the mITT population (1.57 [95% CI: 1.08, 2.28]).

After 60 months of follow-up, the median time to MMR in responders was 9.0 months for bosutinib and 11.9 months for imatinib.

By 60 months, the MMR rates in each Sokal risk group for the bosutinib and imatinib-treated patients, respectively, were 78% and 72% for low risk, 74% and 67% for intermediate risk and 68% and 52% for high risk.

After 60 months of follow-up, 6 (2%) bosutinib patients and 7 (3%) imatinib patients transformed to AP CML or BP CML while on treatment.

At 60 months, the estimated overall survival rate was 95% (95% CI: 91, 97) in the bosutinib group and 94% (95% CI: 90, 96) in the imatinib group.

14.2 Adult Patients with Imatinib-Resistant or -Intolerant Ph+ CP, AP, and BP CML

Study 200 (NCT00261846), a single-arm, open-label, multicenter study in patients with CML who were resistant or intolerant to prior therapy was conducted to evaluate the efficacy and safety of BOSULIF 500 mg once daily in patients with imatinib-resistant or -intolerant CML with separate cohorts for CP, AP, and BP disease previously treated with 1 prior TKI (imatinib) or more than 1 TKI (imatinib followed by dasatinib and/or nilotinib). The definition of imatinib resistance included (1) failure to achieve or maintain any hematologic improvement within 4 weeks; (2) failure to achieve a CHR by 3 months, cytogenetic response by 6 months or major cytogenetic response (MCyR) by 12 months; (3) progression of disease after a previous cytogenetic or hematologic response; or (4) presence of a genetic mutation in the BCR-ABL gene associated with imatinib resistance. Imatinib intolerance was defined as inability to tolerate imatinib due to toxicity, or progression on imatinib and inability to receive a higher dose due to toxicity. The definitions of resistance and intolerance to both dasatinib and nilotinib were similar to those for imatinib. The protocol was amended to exclude patients with a known history of the T315I mutation after 396 patients were enrolled in the trial.

The efficacy endpoints for patients with CP CML previously treated with 1 prior TKI (imatinib) were the rate of attaining MCyR by Week 24 and the duration of MCyR. The efficacy endpoints for patients with CP CML previously treated with both imatinib and at least 1 additional TKI were the cumulative rate of attaining MCyR by Week 24 and the duration of MCyR. The efficacy endpoints for patients with previously treated AP and BP CML were confirmed CHR and overall hematologic response (OHR).

The study enrolled 546 patients with CP, AP or BP CML. Of the total patient population 73% were imatinib resistant and 27% were imatinib intolerant. In this trial, 53% of patients were males, 65% were Caucasian, and 20% were 65 years old or older. Of the 546 treated patients, 506 were considered evaluable for cytogenetic or hematologic efficacy assessment. Patients were evaluable for efficacy if they had received at least 1 dose of BOSULIF and had a valid baseline efficacy assessment. Among evaluable patients, there were 262 patients with CP CML previously treated with 1 prior TKI (imatinib), 112 patients with CP CML previously treated with both imatinib and at least 1 additional TKI, and 132 patients with advanced phase CML previously treated with at least 1 TKI.

Median duration of BOSULIF treatment was 26 months in patients with CP CML previously treated with 1 TKI (imatinib), 9 months in patients with CP CML previously treated with imatinib and at least 1 additional TKI, 10 months in patients with AP CML previously treated with at least imatinib, and 3 months in patients with BP CML previously treated with at least imatinib.

The 24 week efficacy and MCyR at any time results are summarized in Table 14.

Table 14: Efficacy Results in Patients with Ph+ CP CML With Resistance to or Intolerance to Imatinib
 | Prior Treatment With Imatinib Only (N=262 evaluable) n (%) | Prior Treatment With Imatinib and Dasatinib or Nilotinib (N=112 evaluable) n (%)
By Week 24
MCyR | 105 (40.1) | 29 (25.9)
(95% CI) | (34.1, 46.3) | (18.1, 35.0)
MCyR any time | 156 (59.5) | 45 (40.2)
 | (53.3, 65.5) | (31.0, 49.9)
Abbreviations: CI=confidence interval; CML=chronic myelogenous leukemia; CP=chronic phase; MCyR=major cytogenetic response; N/n=number of patients; Ph+=Philadelphia chromosome positive.

The long-term follow-up data analysis was based on a minimum of 60 months for patients with CP CML treated with 1 prior TKI (imatinib) and a minimum of 48 months for patients with CP CML treated with imatinib and at least 1 additional TKI. For the 59.5% of patients with CP CML treated with 1 prior TKI (imatinib) who achieved a MCyR at any time, the median duration of MCyR was not reached. Among these patients, 65.4% and 42.9% had a MCyR lasting at least 18 and 54 months, respectively. For the 40.2% of patients with CP CML treated with imatinib and at least 1 additional TKI who achieved a MCyR at any time, the median duration of MCyR was not reached. Among these patients, 64.4% and 35.6% had a MCyR lasting at least 9 and 42 months, respectively. Of the 403 treated patients with CP CML, 20 patients had confirmed disease transformation to AP or BP while on treatment with BOSULIF.

The 48-week efficacy results in patients with accelerated and blast phases CML previously treated with at least imatinib are summarized in Table 15.

Table 15: Efficacy Results in Patients With Accelerated Phase and Blast Phase CML Previously Treated With at Least Imatinib
 | AP CML (N=72 evaluable) n (%) | BP CML (N=60 evaluable) n (%)
CHR [Overall hematologic response (OHR) = major hematologic response (complete hematologic response + no evidence of leukemia) or return to chronic phase (RCP). All responses were confirmed after 4 weeks. Complete hematologic response (CHR) for AP and BP CML: WBC less than or equal to institutional ULN, platelets greater than or equal to 100,000/mm^3 and less than 450,000/mm^3, absolute neutrophil count (ANC) greater than or equal to 1.0×10^9 /L, no blasts or promyelocytes in peripheral blood, less than 5% myelocytes + metamyelocytes in bone marrow, less than 20% basophils in peripheral blood, and no extramedullary involvement. No evidence of leukemia (NEL): Meets all other criteria for CHR except may have thrombocytopenia (platelets greater than or equal to 20,000/mm^3 and less than 100,000/mm^3) and/or neutropenia (ANC greater than or equal to 0.5×10^9 /L and less than 1.0×10^9 /L). Return to chronic phase (RCP) = disappearance of features defining accelerated or blast phases but still in chronic phase.] by Week 48 | 22 (30.6) | 10 (16.7)
(95% CI) | (20.2, 42.5) | (8.3, 28.5)
OHR by Week 48 | 41 (56.9) | 17 (28.3)
(95% CI) | (44.7, 68.6) | (17.5, 41.4)
Abbreviations: AP=accelerated phase; BP=blast phase; CHR=complete hematologic response; CI=confidence interval; CML=chronic myelogenous leukemia; CI=confidence interval, OHR=overall hematologic response, CHR=complete hematologic response, N/n=number of patients

The long-term follow-up data analysis was based on a minimum of 48 months for patients with AP CML and BP CML. Of the 79 treated patients with AP CML, 3 patients had confirmed disease transformation to BP while on BOSULIF treatment.

14.3 Pediatric Patients with Newly-Diagnosed CP Ph+ CML or with CP Ph+ CML with Resistance or Intolerance to Prior Therapy

The efficacy of BOSULIF in pediatric patients with newly-diagnosed (ND) chronic phase (CP) Ph+ CML and patients with resistant/intolerant (R/I) CP Ph+ CML was evaluated in the BCHILD trial [NCT04258943].

The BCHILD trial is a multicenter, non-randomized, open-label study conducted to identify a recommended dose of bosutinib administered orally once daily in pediatric patients with ND CP Ph+ CML and pediatric patients with R/I CP Ph+ CML who have received at least one prior TKI therapy, to estimate the safety and tolerability and efficacy, and to evaluate the PK of bosutinib in this patient population. The study enrolled 28 patients with R/I CP Ph+ CML treated with BOSULIF at 300 mg/m^2 to 400 mg/m^2 orally once daily, and 21 patients with ND CP Ph+ CML treated at 300 mg/m^2 orally once daily. Efficacy outcomes included CCyR (defined as the absence of Ph+ metaphases in chromosome banding analysis of ≥20 metaphases, or <1% BCR-ABL1–positive nuclei of at least 200 peripheral blood interphase nuclei analyzed by Fluorescence In Situ Hybridization (FISH), or MMR if an adequate cytogenetic assessment was unavailable), MCyR (defined as CCyR or partial cytogenetic response of 1% to 35% Ph+ metaphases), and MMR (defined as ≤0.1% BCR-ABL ratio on international scale [IS]) at any time on study.

Patients with ND CP Ph+ CML had a median age of 14 years (range 5 to 17 years); 68% were male; 81% were White, 14% were Black/African American, and 5% were race not reported.

The major (MCyR) and complete (CCyR) cytogenetic responses among patients with ND CP Ph+ CML were 76.2% (95% CI: 52.8, 91.8) and 71.4% (95% CI: 47.8, 88.7), respectively. The MMR among patients with ND CP Ph+ CML was 28.6% (95% CI: 11.3, 52.3). The median duration of follow-up was 14.2 months (range: 1.1, 26.3 months) in patients with ND CP CML.

Patients with R/I CP Ph+ CML included n=6 treated at 300 mg/m^2 (0.75 times the recommended dose), n=11 treated at 350 mg/m^2 (0.875 times the recommended dose), and n=11 at 400 mg/m^2. Overall (n=28), patients had a median age of 11.5 years (range: 1 to 17 years); 57% were male; 43% were White, 7% were Black/African American, 14% were Asian, and 36% were race not reported.

The major (MCyR) and complete (CCyR) cytogenetic responses among patients with R/I CP Ph+ CML were 82.1% (95% CI: 63.1, 93.9) and 78.6% (95% CI: 59.0, 91.7), respectively. The MMR among patients with R/I CP Ph+ CML was 50.0% (95% CI: 30.6, 69.4). The MR4.5 (defined as BCR-ABL/ABL IS ≤ 0.0032%) was 17.9% (95% CI: 6.1, 36.9). Among 14 patients who achieved MMR, two patients lost MMR after 13.6 months and 24.7 months on treatment. The median duration of follow-up for overall survival was 23.2 months (range: 1.0, 61.5 months) in patients with R/I CP Ph+ CML.

16 HOW SUPPLIED/STORAGE AND HANDLING

Tablets – How Supplied

BOSULIF (bosutinib) tablets are supplied for oral administration in 3 strengths: a 100 mg yellow, oval, biconvex, film-coated tablet debossed with "Pfizer" on one side and "100" on the other; a 400 mg orange, oval, biconvex, film coated tablet debossed with "Pfizer" on one side and "400" on the other; and a 500 mg red, oval, biconvex, film-coated tablet debossed with "Pfizer" on one side and "500" on the other. BOSULIF (bosutinib) tablets are available in the following packaging configurations with a child-resistant (CR) closure (Table 17). Bottles contain a desiccant.

Table 17: Tablet Presentations
BOSULIF Tablets
Package Configuration | Tablet Strength (mg) | NDC | Tablet Description
120 tablets per bottle | 100 mg | 0069-0135-01 | Yellow, oval, biconvex, film-coated tablets, debossed "Pfizer" on one side and "100" on the other.
30 tablets per bottle | 400 mg | 0069-0193-01 | Orange, oval, biconvex, film-coated tablet debossed with "Pfizer" on one side and "400" on the other.
30 tablets per bottle | 500 mg | 0069-0136-01 | Red, oval, biconvex, film-coated tablets, debossed "Pfizer" on one side and "500" on the other.
Abbreviation: NDC=National drug code.

Storage

Store at 20°C to 25°C (68°F to 77°F); excursions permitted to 15°C to 30°C (59°F to 86°F) [see USP Controlled Room Temperature].

Handling and Disposal

Procedures for proper disposal of anticancer drugs should be considered. Touching or handling crushed or broken tablets is to be avoided. Any unused product or waste material should be disposed of in accordance with local requirements, or drug take back programs.

Capsules - How Supplied

BOSULIF (bosutinib) capsules are supplied for oral administration in 2 strengths:

50 mg capsule: size 2 capsule, white body/orange cap with “BOS 50” printed on the body and “Pfizer” printed on the cap in black ink. 100 mg capsule: size 0 capsule, white body/brownish-red cap with “BOS 100” printed on the body and “Pfizer” printed on the cap in black ink. BOSULIF (bosutinib) capsules are available in the following packaging configurations with a CR closure (Table 18).

Table 18: Capsule Presentations
BOSULIF Capsules
Package Configuration Count | Capsule Strength (mg) | NDC | Capsule Description
30 capsules per bottle | 50 | 0069-0504-30 | Size 2 capsule, white body/orange cap with “BOS 50” printed on the body and “Pfizer” printed on the cap in black ink.
150 capsules per bottle | 100 | 0069-1014-15 | Size 0 capsule, white body/brownish-red cap with “BOS 100” printed on the body and “Pfizer” printed on the cap in black ink.
Abbreviation: NDC=National drug code.

Storage

Store at 20°C to 25°C (68°F to 77°F); excursions permitted to 15°C to 30°C (59°F to 86°F) [see USP Controlled Room Temperature] and Store and Dispense in Original Container.

Handling and Disposal

Procedures for proper disposal of anticancer drugs should be considered. Patients and/or caregivers must wear gloves while handling the drug product, and wash their hands once finished. Any unused product or waste material should be disposed of in accordance with local requirements.

17 PATIENT COUNSELING INFORMATION

Advise the patient to read the FDA-approved patient labeling (Patient Information and Instructions for Use).

- Dosage and Administration

Instruct patients to take BOSULIF exactly as prescribed, not to change their dose or to stop taking BOSULIF unless they are told to do so by their doctor. If patients miss a dose beyond 12 hours, they should be advised to take the next scheduled dose at its regular time. A double dose should not be taken to make up for any missed dose. Advise patients to take BOSULIF with food. Patients should be advised: “Swallow tablets whole. Do not crush, break, or cut tablet. Do not touch or handle crushed or broken tablets.” Patients should be advised: “Capsules may be swallowed whole. For those that cannot swallow the capsule whole, the capsule can be opened and the contents mixed with applesauce or yogurt.”

- Gastrointestinal Toxicity

Advise patients that they may experience diarrhea, nausea, vomiting, abdominal pain, or blood in their stools with BOSULIF and to seek medical attention promptly for these symptoms [see Warnings and Precautions (5.1)].

- Myelosuppression

Advise patients of the possibility of developing low blood cell counts and to immediately report fever, any suggestion of infection, or signs or symptoms suggestive of bleeding or easy bruising [see Warnings and Precautions (5.2)].

- Hepatic Toxicity

Advise patients of the possibility of developing liver function abnormalities and to immediately report jaundice [see Warnings and Precautions (5.3)].

- Cardiovascular Toxicity

Advise patients that cardiac failure, left ventricular dysfunction, and cardiac ischemic events have been reported. Advise patients to seek immediate medical attention if any symptoms suggestive of cardiac failure and cardiac ischemia occur, such as shortness of breath, weight gain, or fluid retention [see Warnings and Precautions (5.4)].

- Fluid Retention

Advise patients of the possibility of developing fluid retention (swelling, weight gain, or shortness of breath) and to seek medical attention promptly if these symptoms arise [see Warnings and Precautions (5.5)].

- Renal Toxicity

Advise patients of the possibility of developing renal problems and to immediately report frequent urination, polyuria or oliguria [see Warnings and Precautions (5.6)].

- Adverse Reactions

Advise patients that they may experience other adverse reactions such as respiratory tract infections, rash, fatigue, loss of appetite, headache, dizziness, back pain, arthralgia, pruritus or constipation with BOSULIF and to seek medical attention if symptoms are significant. There is a possibility of anaphylactic shock [see Contraindications (4) and Adverse Reactions (6)].

- Embryo-Fetal Toxicity

Advise females to inform their healthcare provider if they are pregnant or become pregnant. Advise female patients of the risk to a fetus and potential loss of the pregnancy [see Use in Specific Populations (8.1)].

Advise females of reproductive potential, to use effective contraception during treatment and for 2 weeks after receiving the last dose of BOSULIF [see Warnings and Precautions (5.7) and Use in Specific Populations (8.1, 8.3)].

Advise lactating women not to breastfeed during treatment with BOSULIF and for 2 weeks after the last dose [see Use in Specific Populations (8.2)].

- Drug Interactions

Advise patients that BOSULIF and certain other medicines, including over the counter medications or herbal supplements (such as St. John's wort) can interact with each other and may alter the effects of BOSULIF [see Drug Interactions (7)].

LAB-0443-19.0

PATIENT INFORMATION

BOSULIF® (BAH-su-lif)

(bosutinib)

tablets

BOSULIF® (BAH-su-lif)

(bosutinib)

capsules

What is BOSULIF?
BOSULIF is a prescription medicine used to treat:

- adults and children 1 year of age and older who have a certain type of leukemia called chronic phase (CP) Philadelphia chromosome-positive chronic myelogenous leukemia (Ph+ CML) who are newly-diagnosed or who no longer benefit from or did not tolerate other treatment.
- adults with accelerated phase (AP), or blast phase (BP) Ph+ CML who can no longer benefit from or did not tolerate other treatment.

It is not known if BOSULIF is safe and effective in children less than 1 year of age with CP Ph+ CML who are newly‑diagnosed or who no longer benefit from or did not tolerate other treatment or in children with AP Ph+ CML or BP Ph+ CML.

Do not take BOSULIF if you are allergic to bosutinib or any of the ingredients in BOSULIF. See the end of this leaflet for a complete list of ingredients of BOSULIF.

Before taking BOSULIF, tell your doctor about all of your medical conditions, including if you:

- have liver problems
- have heart problems
- have kidney problems
- have high blood pressure
- have diabetes
- are pregnant or plan to become pregnant. BOSULIF can harm your unborn baby. Females who are able to become pregnant should have a pregnancy test before starting treatment with BOSULIF. Tell your doctor right away if you become pregnant during treatment with BOSULIF.
  - Females who are able to become pregnant should use effective birth control (contraception) during treatment with BOSULIF and for 2 weeks after the last dose. Talk to your doctor about birth control methods that may be right for you.
- are breastfeeding or plan to breastfeed. It is not known if BOSULIF passes into your breast milk or if it can harm your baby. Do not breastfeed during treatment with BOSULIF and for 2 weeks after the last dose.

Tell your doctor about all the medicines you take, including prescription medicines, over-the-counter medicines, vitamins, and herbal supplements. When taken together, BOSULIF and certain other medicines can affect each other.
Know the medicines you take. Keep a list of your medicines and show it to your doctor and pharmacist when you get a new medicine.

How should I take BOSULIF?

- Take BOSULIF exactly as prescribed by your doctor.
- Do not change your dose or stop taking BOSULIF without first talking with your doctor.
- If your child takes BOSULIF, your healthcare provider will change the dose as your child grows.
- Take BOSULIF with food.
- Swallow BOSULIF tablets whole. Do not crush, break, chew or cut BOSULIF tablets. Do not touch or handle crushed or broken BOSULIF tablets.
- Swallow BOSULIF capsules whole. If you cannot swallow BOSULIF capsules whole, tell your healthcare provider.
- If you cannot swallow BOSULIF capsules whole, see the “Instructions for Use” for detailed instructions on how to prepare and give a dose of BOSULIF capsules by opening the capsules and mixing the capsule contents with applesauce or yogurt.
- If you take an antacid or H2 blocker medicine, take it at least 2 hours before or 2 hours after BOSULIF. If you take a Proton Pump Inhibitor (PPI) medicine, talk to your doctor or pharmacist.
- You should avoid grapefruit, grapefruit juice, and supplements that contain grapefruit extract during treatment with BOSULIF. Grapefruit products increase the amount of BOSULIF in your body.
- If you miss a dose of BOSULIF, take it as soon as you remember. If you miss a dose by more than 12 hours, skip that dose and take your next dose at your regular time. Do not take 2 doses at the same time.
- If you take too much BOSULIF, call your doctor or go to the nearest hospital emergency room right away.

What are the possible side effects of BOSULIF?
BOSULIF may cause serious side effects, including:

- Stomach problems. BOSULIF may cause stomach (abdomen) pain, nausea, diarrhea, vomiting, or blood in your stools. Get medical help right away for any stomach problems.
- Low blood cell counts. BOSULIF may cause low platelet counts (thrombocytopenia), low red blood cell counts (anemia) and low white blood cell counts (neutropenia). Your doctor should do blood tests to check your blood cell counts regularly during your treatment with BOSULIF. Call your doctor right away if you have unexpected bleeding or bruising, blood in your urine or stools, fever, or any signs of an infection.
- Liver problems. Your doctor should do blood tests to check your liver function regularly during your treatment with BOSULIF. Call your doctor right away if your skin or the white part of your eyes turns yellow (jaundice) or you have dark "tea color" urine.
- Heart problems. BOSULIF may cause heart problems, including heart failure and decreased blood flow to the heart which can lead to heart attack. Get medical help right away if you get shortness of breath, weight gain, chest pain, or swelling in your hands, ankles or feet.
- Your body may hold too much fluid (fluid retention). Fluid may build up in the lining of your lungs, the sac around your heart, or your stomach cavity. Get medical help right away if you get any of the following symptoms during your treatment with BOSULIF:

- shortness of breath and cough
- chest pain
- swelling in your hands, ankles, or feet

- swelling all over your body
- weight gain

- Kidney problems. Your doctor should do tests to check your kidney function when you start treatment with BOSULIF and during your treatment. Call your doctor right away if you get any of the following symptoms during your treatment with BOSULIF:
  - you urinate more often than normal
  - you urinate less often than normal
  - you make a much larger amount of urine than normal
  - you make a much smaller amount of urine than normal

The most common side effects of BOSULIF in adults and children with CML include:

- diarrhea
- stomach (abdominal) pain
- vomiting
- nausea
- rash
- tiredness
- liver problems

- headache
- fever
- decreased appetite
- respiratory tract infections (infections in nose, throat or lungs)
- constipation
- changes in certain blood tests. Your doctor may do blood tests during treatment with BOSULIF to check for changes

Tell your doctor or get medical help right away if you get respiratory tract infections, loss of appetite, headache, dizziness, back pain, joint pain, rash or itching while taking BOSULIF. These may be symptoms of a severe allergic reaction.
Your doctor may change your dose, temporarily stop, or permanently stop treatment with BOSULIF if you have certain side effects.
BOSULIF may cause fertility problems in females and males. This may affect your ability to have a child. Talk to your doctor if this is a concern for you.
Tell your doctor if you have any side effect that bothers you or that does not go away.
These are not all of the possible side effects of BOSULIF.
Call your doctor for medical advice about side effects. You may report side effects to FDA at 1-800-FDA-1088.

How should I store BOSULIF?

- Store BOSULIF tablets and capsules at room temperature between 68°F to 77°F (20°C to 25°C).
- The BOSULIF tablets and capsules bottle has a child-resistant closure.
- The BOSULIF tablets bottle contains a desiccant to help keep your medicine dry (protect it from moisture). Keep the desiccant in the bottle. Do not eat the desiccant.
- Store the BOSULIF capsules in the original bottle.
- Ask your doctor or pharmacist about the right way to throw away outdated or unused BOSULIF.

Keep BOSULIF and all medicines out of the reach of children.

General information about the safe and effective use of BOSULIF.
Medicines are sometimes prescribed for purposes other than those listed in a Patient Information leaflet. Do not use BOSULIF for a condition for which it is not prescribed. Do not give BOSULIF to other people even if they have the same symptoms you have. It may harm them. You can ask your doctor or pharmacist for information about BOSULIF that is written for health professionals.

What are the ingredients in BOSULIF?
Active ingredient: bosutinib.
Inactive ingredients: Tablets: croscarmellose sodium, iron oxide red (for 400 mg, and 500 mg tablet) and iron oxide yellow (for 100 mg, and 400 mg tablet), magnesium stearate, microcrystalline cellulose, poloxamer, polyethylene glycol, polyvinyl alcohol, povidone, talc and titanium dioxide. Capsules: croscarmellose sodium, gelatin, magnesium stearate, mannitol, microcrystalline cellulose, poloxamer, povidone, red iron oxide, titanium dioxide, yellow iron oxide. The printing ink contains black iron oxide, potassium hydroxide, propylene glycol, shellac, strong ammonia solution.

For more information, go to www.Bosulif.com or www.pfizermedicalinformation.com or call 1-800-438-1985.

This Patient Information has been approved by the U.S. Food and Drug Administration. Revised 12/2024

INSTRUCTIONS FOR USE

BOSULIF® (BAH-su-lif)

(bosutinib)

capsules

This Instructions for Use contains information on how to prepare and give a dose of BOSULIF capsules by opening the capsules and mixing the contents with applesauce or yogurt for people who cannot swallow capsules whole. Read this Instructions for Use before you prepare or give the first dose of BOSULIF, and each time you get a refill. Ask your healthcare provider or pharmacist if you have any questions.

Important information you need to know before preparing a dose of BOSULIF capsules:

- BOSULIF capsules can be opened and the capsules contents mixed with room temperature applesauce or yogurt.
- Only use applesauce or yogurt. Do not mix BOSULIF with other foods.
- Swallow all of the mixture right away, without chewing. Do not store the mixture for later use.
- If you do not swallow the entire BOSULIF mixture, do not mix another dose. Wait until the next day to take your regularly scheduled dose.
- Take the BOSULIF mixture with a full meal.

Preparing a dose of BOSULIF capsules:

Gather the following supplies:

- BOSULIF capsules
- small, clean container
- yogurt or applesauce
- teaspoon for mixing
- disposable gloves

Giving a dose of BOSULIF capsules:

Step 1: Choose a clean, flat work surface. Place all supplies on the work surface.

Step 2: Wash and dry your hands well.

Step 3: Put on disposable gloves

Step 4: Get the prescribed number of BOSULIF capsule(s) needed to prepare the dose.

Step 5: Add the amount of applesauce or yogurt needed for the prescribed dose to the container.

Dose | Amount of Applesauce or Yogurt
100 mg | 10 mL (2 teaspoons)
150 mg | 15 mL (3 teaspoons)
200 mg | 20 mL (4 teaspoons)
250 mg | 25 mL (5 teaspoons)
300 mg | 30 mL (6 teaspoons)
350 mg | 30 mL (6 teaspoons)
400 mg | 35 mL (7 teaspoons)
450 mg | 40 mL (8 teaspoons)
500 mg | 45 mL (9 teaspoons)
550 mg | 45 mL (9 teaspoons)
600 mg | 50 mL (10 teaspoons)

Step 6: Carefully open each of the BOSULIF capsule(s) needed for the dose and empty the entire contents into the applesauce or yogurt. Mix the entire capsule contents with the applesauce or yogurt in the container.

Step 7: Swallow all of the mixture right away, without chewing.

Step 8: Dispose of (throw away) the empty BOSULIF capsule shell(s) in the household trash.

Step 9: Wash teaspoon and the container with soap and warm water.

Step 10: Remove disposable gloves and throw them away in the household trash.

Step 11: Wash and dry your hands.

How should I store BOSULIF capsules?

- Store BOSULIF at room temperature between 68°F to 77°F (20°C to 25°C).
- Store the BOSULIF capsules in the original bottle.
- Ask your doctor or pharmacist about the right way to throw away outdated or unused BOSULIF.

Keep BOSULIF and all medicines out of the reach of children.

LAB-0639-13.0
For more information, go to www.Bosulif.com or www.pfizermedicalinformation.com or call 1-800-438-1985.
This Instructions for Use has been approved by the U.S. Food and Drug Administration.
Issued: 9 2023

PRINCIPAL DISPLAY PANEL - 100 mg Bottle Label

NDC 0069-0135-01

Pfizer

Bosulif®
(bosutinib) tablets

100 mg

Do not crush or cut tablet
For Oncology Use Only

120 Tablets

Rx only

PRINCIPAL DISPLAY PANEL - 500 mg Bottle Label

NDC 0069-0136-01

Pfizer

Bosulif®
(bosutinib) tablets

500 mg

Do not crush or cut tablet
For Oncology Use Only

30 Tablets

Rx only

PRINCIPAL DISPLAY PANEL - 400 mg Tablet Bottle Label

NDC 0069-0193-01

Pfizer

Bosulif®
(bosutinib) tablets

400 mg

Do not crush or cut tablet
For Oncology Use Only

30 Tablets

Rx only

PRINCIPAL DISPLAY PANEL - 50 mg Capsule Bottle Label

NDC 0069-0504-30

Pfizer

Bosulif®
(bosutinib) capsules

50 mg

For Oncology Use Only
Attention: Store and dispense
Bosulif in original container.

30 Capsules

Rx only

PRINCIPAL DISPLAY PANEL - 100 mg Capsule Bottle Label

NDC 0069-1014-15

Pfizer

Bosulif®
(bosutinib) capsules

100 mg

For Oncology Use Only
Attention: Store and dispense
Bosulif in original container.

150 Capsules

Rx only